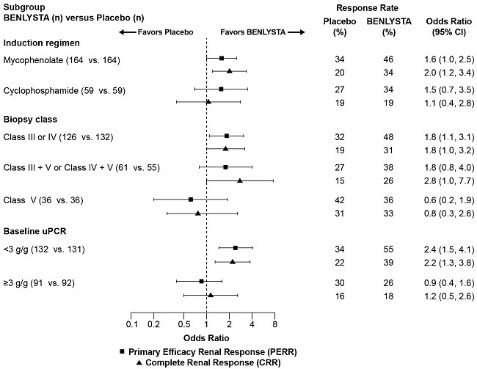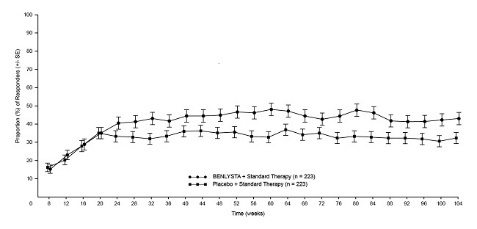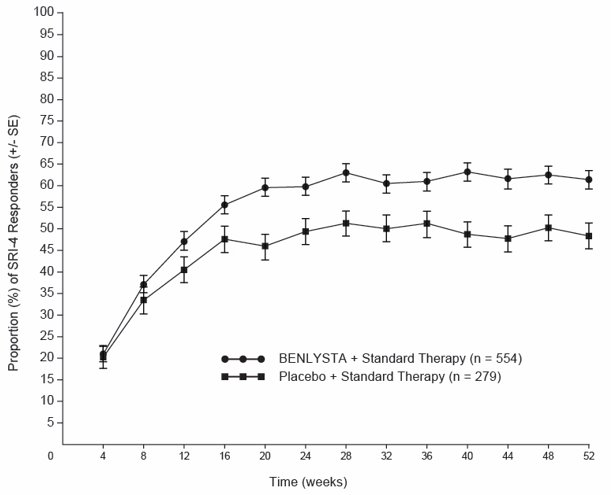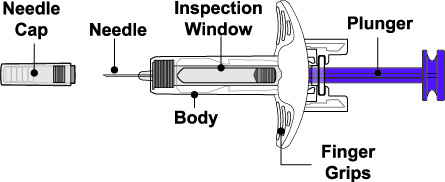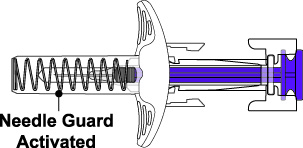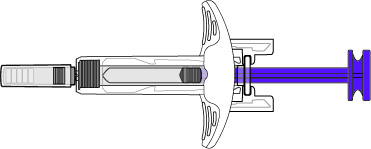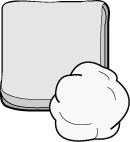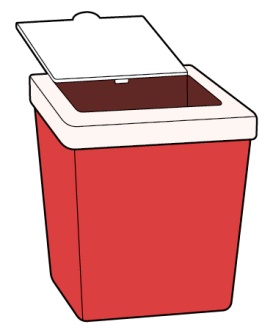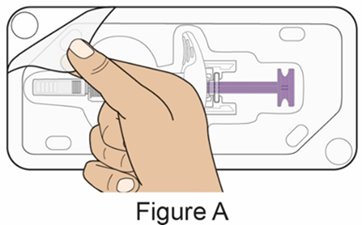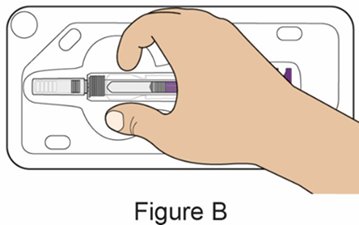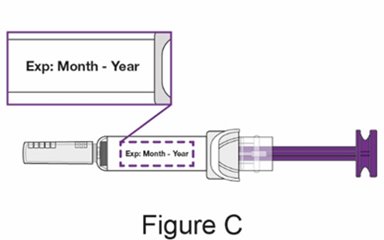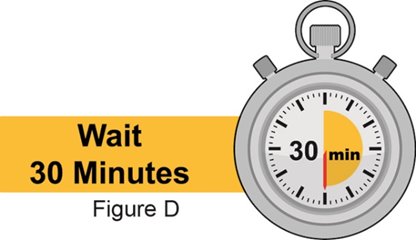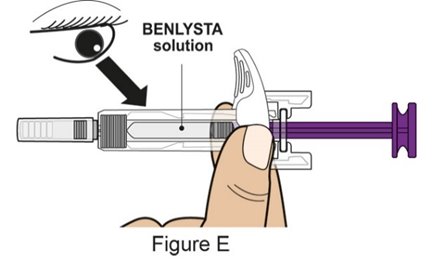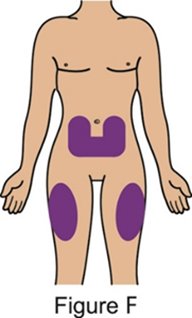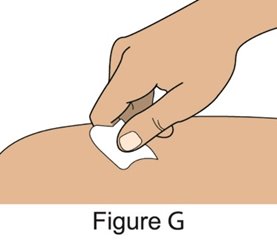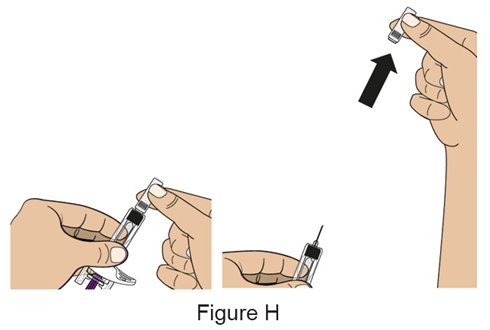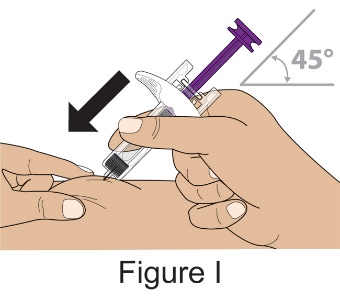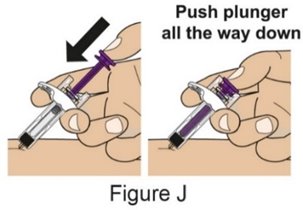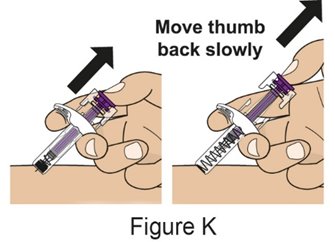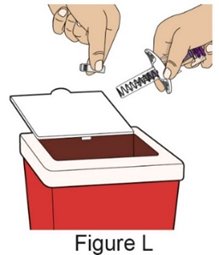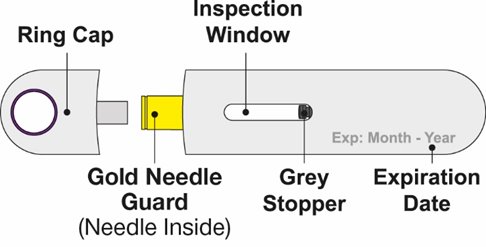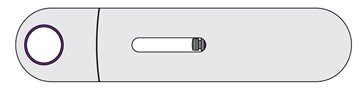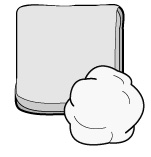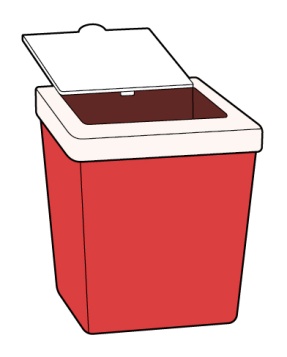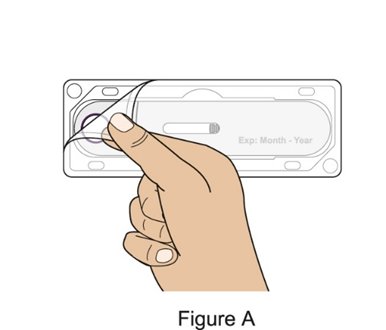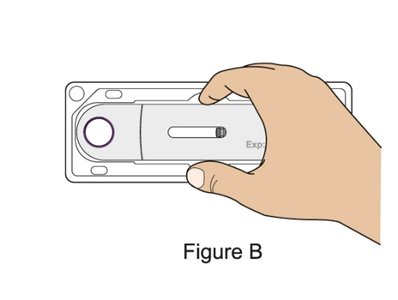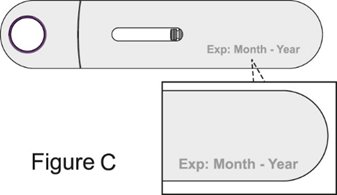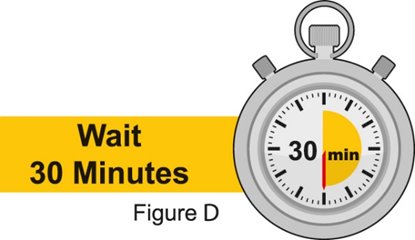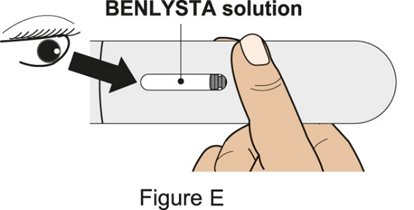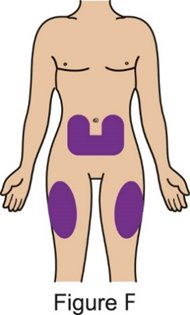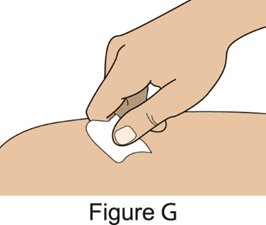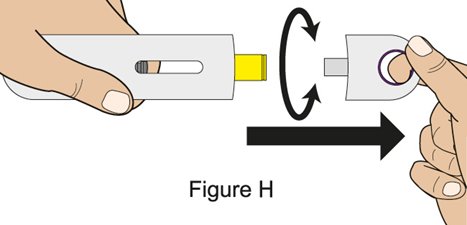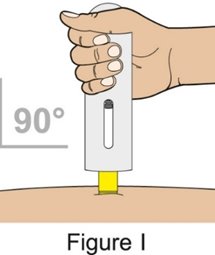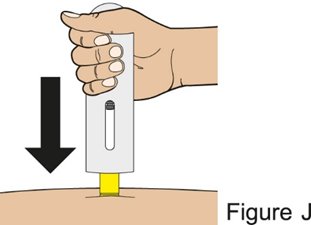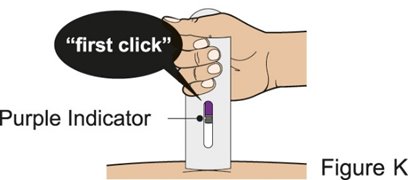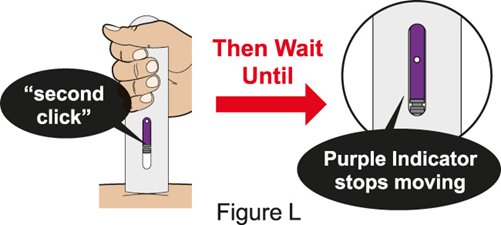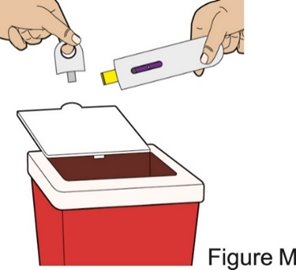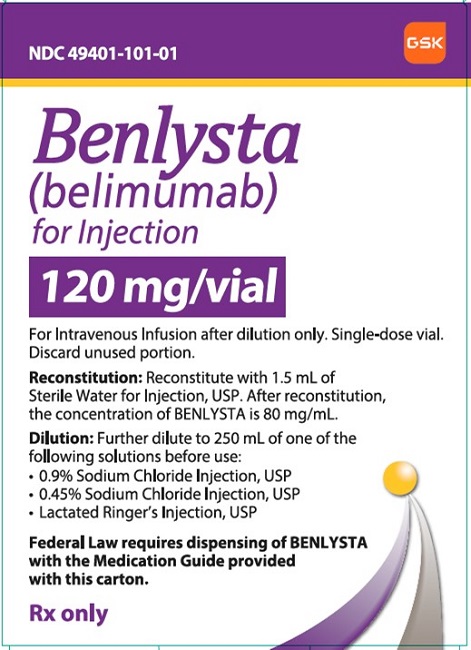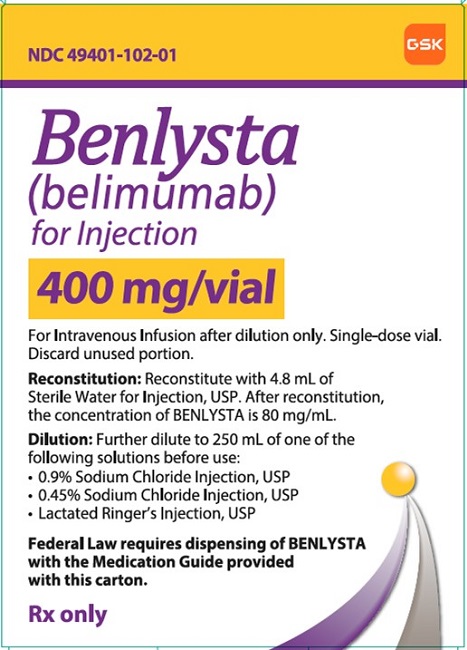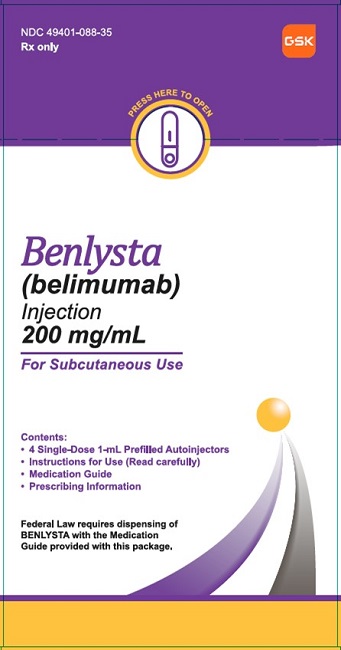 DRUG LABEL: BENLYSTA
NDC: 49401-102 | Form: INJECTION, POWDER, LYOPHILIZED, FOR SOLUTION
Manufacturer: GlaxoSmithKline LLC
Category: prescription | Type: HUMAN PRESCRIPTION DRUG LABEL
Date: 20250620

ACTIVE INGREDIENTS: BELIMUMAB 400 mg/5 mL
INACTIVE INGREDIENTS: SODIUM CITRATE, UNSPECIFIED FORM; POLYSORBATE 80; CITRIC ACID MONOHYDRATE; SUCROSE

HIGHLIGHTS OF PRESCRIBING INFORMATION

These highlights do not include all the information needed to use BENLYSTA safely and effectively. See full prescribing information for BENLYSTA.
BENLYSTA (belimumab) for injection, for intravenous use
BENLYSTA (belimumab) injection, for subcutaneous use
Initial U.S. Approval: 2011

RECENT MAJOR CHANGES

Dosage and Administration (2.3, 2.4) | 6/2025

1 INDICATIONS AND USAGE

BENLYSTA is a B-lymphocyte stimulator (BLyS)-specific inhibitor indicated for the treatment of patients 5 years of age and older with:

- Active systemic lupus erythematosus (SLE) who are receiving standard therapy; (1)
- Active lupus nephritis who are receiving standard therapy. (1)

Limitations of Use:

The efficacy of BENLYSTA has not been evaluated in patients with severe active central nervous system lupus. Use of BENLYSTA is not recommended in this situation. (1)

2 DOSAGE AND ADMINISTRATION

- See Full Prescribing Information for complete preparation and administration information. (2.1, 2.2, 2.3)
- Intravenous dosage for active SLE or lupus nephritis:
  - 10 mg/kg at 2‑week intervals for the first 3 doses and at 4‑week intervals thereafter.
  - Reconstitute, dilute, and administer as an intravenous infusion over a period of 1 hour. (2.2)
  - Consider prophylactic premedication for infusion reactions and hypersensitivity reactions. (2.1, 2.2)
- Subcutaneous dosage for active SLE or lupus nephritis: (2.3)

Indication | Adults (Autoinjector or Prefilled Syringe) | Pediatric Patients 5 Years of Age and Older; (Weight‑Based Dosing); (Autoinjector Only)a
Active SLE | 200 mg once weekly | - ≥40 kg: 200 mg once weekly - 15 kg to less than 40 kg: 200 mg once every 2 weeks
Active Lupus Nephritis | 400 mgb once weekly for 4 doses, followed by 200 mg once weekly | - ≥40 kg: 400 mgb once weekly for 4 doses, followed by 200 mg once weekly - 15 kg to less than 40 kg: 200 mg once weekly for 4 doses, followed by 200 mg once every 2 weeks
a Prefilled syringe has not been studied in children less than 18 years of age.
b The 400-mg dose requires administration of two 200‑mg injections.

3 DOSAGE FORMS AND STRENGTHS

- Intravenous Infusion (for injection): 120 mg or 400 mg of belimumab lyophilized powder in single‑dose vial for reconstitution and dilution prior to intravenous infusion. (3)
- Subcutaneous Injection (injection): 200 mg/mL of belimumab in single‑dose prefilled autoinjector or single‑dose prefilled syringe. (3)

4 CONTRAINDICATIONS

Previous anaphylaxis to belimumab. (4)

5 WARNINGS AND PRECAUTIONS

- Serious Infections: Serious and sometimes fatal infections have occurred in patients receiving immunosuppressive agents, including BENLYSTA. Use with caution in patients with severe or chronic infections. Consider interrupting therapy with BENLYSTA if patients develop a new infection during treatment with BENLYSTA. (5.1)
- Progressive Multifocal Leukoencephalopathy (PML): Evaluate patients with new-onset or deteriorating neurological signs and symptoms for PML. If PML is suspected, immunosuppressant therapy, including BENLYSTA, must be suspended until PML has been excluded. If PML is confirmed, immunosuppressant therapy, including BENLYSTA, must be discontinued. (5.1)
- Hypersensitivity Reactions, including Anaphylaxis: Serious and fatal reactions have been reported. (5.2)
- Depression and Suicidality: Depression and suicidality were reported in trials with BENLYSTA. Assess for depression and risk of suicide before treatment with BENLYSTA and monitor during treatment. Instruct patients to contact their healthcare provider if new or worsening depression, suicidal thoughts, or other mood changes occur. (5.3)
- Immunization: Live vaccines should not be given concurrently with BENLYSTA. (5.5)

6 ADVERSE REACTIONS

Common adverse reactions (≥5%): nausea, diarrhea, pyrexia, nasopharyngitis, bronchitis, insomnia, pain in extremity, depression, migraine, pharyngitis, and injection site reactions (subcutaneous administration). (6.1)

To report SUSPECTED ADVERSE REACTIONS, contact GlaxoSmithKline at 1-877-423-6597 or FDA at 1-800-FDA-1088 or www.fda.gov/medwatch.

FULL PRESCRIBING INFORMATION

1 INDICATIONS AND USAGE

BENLYSTA is indicated for the treatment of patients 5 years of age and older with:

- Active systemic lupus erythematosus (SLE) who are receiving standard therapy, and
- Active lupus nephritis who are receiving standard therapy.

Limitations of Use

The efficacy of BENLYSTA has not been evaluated in patients with severe active central nervous system (CNS) lupus. Use of BENLYSTA is not recommended in this situation.

2 DOSAGE AND ADMINISTRATION

2.1 Important Administration Instructions

BENLYSTA may be administered intravenously or subcutaneously [see Dosage and Administration (2.2, 2.3)]. Vials are intended for intravenous use only (not for subcutaneous use) and autoinjectors and prefilled syringes are intended for subcutaneous use only (not for intravenous use).

Precautions Prior to Intravenous Use

BENLYSTA should be administered by healthcare providers prepared to manage anaphylaxis [see Warnings and Precautions (5.2)].

Prior to intravenous dosing with BENLYSTA, consider administering premedication for prophylaxis against infusion reactions and hypersensitivity reactions [see Warnings and Precautions (5.2), Adverse Reactions (6.1)].

2.2 Recommended Intravenous Dosage, and Preparation and Administration Instructions

BENLYSTA for intravenous use must be reconstituted and diluted prior to administration. Do not administer as an intravenous push or bolus.

Recommended Dosage and Administration

The recommended intravenous BENLYSTA dosage in patients 5 years of age and older with active SLE or lupus nephritis is 10 mg/kg at 2‑week intervals for the first 3 doses and at 4‑week intervals thereafter.

Reconstitute, dilute, and administer as an intravenous infusion over a period of 1 hour. Do not concomitantly infuse BENLYSTA in the same intravenous line with other agents. No physical or biochemical compatibility studies have been conducted to evaluate the coadministration of BENLYSTA with other agents.

The infusion rate may be slowed or interrupted if the patient develops an infusion reaction. The infusion must be discontinued immediately if the patient experiences a serious hypersensitivity reaction [see Contraindications (4), Warnings and Precautions (5.2)].

Preparation of the Intravenous Solution

BENLYSTA for intravenous use is provided as a lyophilized powder in a single‑dose vial and should be reconstituted and diluted by a healthcare professional using aseptic technique as follows. Use of a 21- to 25-gauge needle is recommended when piercing the vial stopper for reconstitution and dilution.

Reconstitution Instructions for Intravenous Use:

1. Remove the vial of BENLYSTA from the refrigerator and allow to stand for 10 to 15 minutes for the vial to reach room temperature.
2. Reconstitute the BENLYSTA powder with Sterile Water for Injection, USP, as follows. The reconstituted solution will contain a concentration of 80 mg/mL belimumab.
3. Reconstitute the 120-mg vial with 1.5 mL Sterile Water for Injection, USP.
4. Reconstitute the 400-mg vial with 4.8 mL Sterile Water for Injection, USP.
3. Direct the stream of sterile water towards the side of the vial to minimize foaming. Gently swirl the vial for 60 seconds. Allow the vial to sit at room temperature during reconstitution, gently swirling the vial for 60 seconds every 5 minutes until the powder is dissolved. Do not shake. Reconstitution is typically complete within 10 to 15 minutes after the sterile water has been added, but it may take up to 30 minutes. Protect the reconstituted solution from sunlight.
4. If a mechanical reconstitution device (swirler) is used to reconstitute BENLYSTA, do not exceed 500 rpm or swirl the vial for more than 30 minutes.
5. Once reconstitution is complete, the solution should be opalescent and colorless to pale yellow, and without particles. Small air bubbles, however, are expected and acceptable.

Dilution Instructions for Intravenous Use:

1. Dextrose intravenous solutions are incompatible with BENLYSTA. BENLYSTA should only be diluted in 0.9% Sodium Chloride Injection, USP (normal saline), 0.45% Sodium Chloride Injection, USP (half-normal saline), or Lactated Ringer’s Injection, USP to a volume of 250 mL for intravenous infusion. To prepare the intravenous infusion solution for patients whose body weight is less than or equal to 40 kg, a 100 mL bag or bottle of normal saline, half-normal saline, or Lactated Ringer’s Injection may be used such that the resulting belimumab concentration in the infusion bag does not exceed 4 mg/mL. From a 250‑mL (or 100‑mL) infusion bag or bottle of normal saline, half-normal saline, or Lactated Ringer’s Injection, withdraw and discard a volume equal to the volume of the reconstituted solution of BENLYSTA required for the patient’s dose. Then add the required volume of the reconstituted solution of BENLYSTA into the intravenous infusion solution in the infusion bag or bottle. Gently invert the bag or bottle to mix the intravenous infusion solution. Any unused solution in the vials must be discarded.
2. Visually inspect parenteral drug products for particulate matter and discoloration prior to administration, whenever solution and container permit. Discard the solution if any particulate matter or discoloration is observed.
3. If the reconstituted solution of BENLYSTA is not used immediately, store, protect from direct sunlight and refrigerate at 36°F to 46°F (2°C to 8°C). Store solutions of BENLYSTA diluted in normal saline, half‑normal saline, or Lactated Ringer’s Injection at 36°F to 46°F (2°C to 8°C) or room temperature. The total time from reconstitution of BENLYSTA to completion of infusion should not exceed 8 hours.
4. No incompatibilities between BENLYSTA and polyvinylchloride or polyolefin bags have been observed.

2.3 Recommended Subcutaneous Dosage, and Preparation and Administration Instructions

The recommended subcutaneous BENLYSTA dosage in patients 5 years of age and older with active SLE or lupus nephritis is provided in Table 1. Administer BENLYSTA subcutaneously in the abdomen or thigh. For patients less than 10 years of age, BENLYSTA must be administered by a healthcare professional or trained caregiver.

Table 1. Recommended Subcutaneous Dosage of BENLYSTA
Indication | Adults; (Autoinjector or Prefilled Syringe) | Pediatric Patients 5 Years of Age and Older; (Weight‑Based Dosing); (Autoinjector Only)a
Active SLE | 200 mg once weekly | - Patients greater than or equal to 40 kg: 200 mg once weekly - Patients 15 kg to less than 40 kg: 200 mg once every 2 weeks
Active Lupus Nephritis | 400 mgb once weekly for 4 doses, followed by 200 mg once weekly | - Patients greater than or equal to 40 kg: 400 mgb once weekly for 4 doses, followed by 200 mg once weekly - Patients 15 kg to less than 40 kg: 200 mg once weekly for 4 doses, followed by 200 mg once every 2 weeks
a The prefilled syringe has not been studied in pediatric patients less than 18 years of age.
b The 400-mg dose requires administration of two 200-mg injections.

Administration Instructions for Subcutaneous Injection

1. Administer the first subcutaneous injection of BENLYSTA under the supervision of a healthcare provider. Provide patients or caregivers with proper training on subcutaneous administration and education about signs and symptoms of hypersensitivity reactions [see Warnings and Precautions (5.2)]. For adults and pediatric patients 10 years of age and older, subsequent subcutaneous BENLYSTA administrations may be performed by the patient or trained caregiver, if determined to be appropriate. For pediatric patients less than 10 years of age, subsequent subcutaneous BENLYSTA administrations must be performed by a healthcare provider or trained caregiver.
2. Instruct the patient or caregiver to follow the directions for administration provided in the Instructions for Use.
3. Instruct the patient or caregiver to remove the autoinjector or prefilled syringe from the refrigerator and allow it to sit at room temperature for 30 minutes prior to the subcutaneous injection. Do not warm BENLYSTA in any other way.
4. Prior to administration, instruct the patient or caregiver to visually inspect the window of the autoinjector or the prefilled syringe for particulate matter or discoloration. BENLYSTA should be clear to opalescent and colorless to pale yellow. Do not use BENLYSTA if the product exhibits discoloration or particulate matter. Instruct the patient or caregiver not to use the BENLYSTA autoinjector or prefilled syringe if dropped on a hard surface.
5. When injecting in the same body region, advise the patient or caregiver to use a different injection site for each injection; never give injections into areas where the skin is tender, bruised, red, or hard. When administering a 400‑mg dose, inject each 200‑mg injection at least 5 cm (approximately 2 inches) apart.
6. Instruct the patient or caregiver to administer BENLYSTA, preferably on the same day each week or the same day of alternate weeks, as appropriate.
7. If a dose is missed, instruct the patient or caregiver to administer a dose as soon as the patient remembers. Thereafter, the patient can resume dosing on their usual day of administration or start a new schedule from the day that the missed dose was administered.

2.4 Switching from Intravenous to Subcutaneous BENLYSTA Use

Active SLE

Administer the first subcutaneous BENLYSTA dose 1 to 4 weeks after the last intravenous dose. To switch:

- Adults and pediatric patients greater than or equal to 40 kg, administer the first 200 mg subcutaneous dose 1 to 4 weeks after the last intravenous dose, then continue 200 mg subcutaneous dosing once weekly.
- Pediatric patients 15 kg to less than 40 kg, administer the first 200 mg subcutaneous dose 1 to 4 weeks after the last intravenous dose, then continue 200 mg subcutaneous dosing every 2 weeks.

Active Lupus Nephritis

Patients may be switched from intravenous BENLYSTA treatment to subcutaneous BENLYSTA treatment after completing at least 2 intravenous doses. To switch:

- Adults and pediatric patients greater than or equal to 40 kg, administer the first 200 mg subcutaneous dose 1 to 2 weeks after the last intravenous dose, then continue 200 mg subcutaneous dosing once weekly.
- Pediatric patients 15 kg to less than 40 kg, administer the first 200 mg subcutaneous dose 1 to 2 weeks after the last intravenous dose, then continue 200 mg subcutaneous dosing every 2 weeks.

3 DOSAGE FORMS AND STRENGTHS

Intravenous Infusion

For injection: 120 mg or 400 mg of belimumab as a lyophilized powder in single‑dose vials for reconstitution and dilution prior to intravenous infusion.

Subcutaneous Injection

Injection: 200 mg/mL of belimumab as a clear to opalescent and colorless to pale yellow solution in a single-dose prefilled autoinjector or a single-dose prefilled glass syringe.

4 CONTRAINDICATIONS

BENLYSTA is contraindicated in patients who have had anaphylaxis with belimumab.

5 WARNINGS AND PRECAUTIONS

5.1 Serious Infections

Serious and sometimes fatal infections have been reported in patients receiving immunosuppressive agents, including BENLYSTA. Overall, the incidence of serious infections in controlled trials was similar in subjects receiving BENLYSTA compared with placebo, whereas fatal infections occurred more frequently in subjects receiving BENLYSTA [see Adverse Reactions (6.1)].

Consider the risk and benefit before initiating treatment with BENLYSTA in patients with severe or chronic infections. Consider interrupting therapy with BENLYSTA in patients who develop a new infection while receiving it and monitor these patients closely.

Progressive Multifocal Leukoencephalopathy (PML)

Cases of JC virus-associated PML resulting in neurological deficits, including fatal cases, have been reported in patients with SLE receiving immunosuppressants, including BENLYSTA. Risk factors for PML include treatment with immunosuppressant therapies and impairment of immune function. Consider the diagnosis of PML in any patient presenting with new-onset or deteriorating neurological signs and symptoms and consult with a neurologist or other appropriate specialist as clinically indicated. In patients with suspected PML, immunosuppressant therapy, including BENLYSTA, must be suspended until PML has been excluded. If PML is confirmed, immunosuppressant therapy, including BENLYSTA, must be discontinued.

5.2 Hypersensitivity Reactions, including Anaphylaxis

Acute hypersensitivity reactions, including anaphylaxis and death, and infusion-related reactions have been reported in association with BENLYSTA [see Adverse Reactions (6.1)]. These events generally occurred within hours of the infusion; however, they may occur later. Non-acute hypersensitivity reactions including rash, nausea, fatigue, myalgia, headache, and facial edema have been reported and typically occurred up to a week following the most recent infusion. Hypersensitivity, including serious reactions, has occurred in patients who have previously tolerated infusions of BENLYSTA. Limited data suggest that patients with a history of multiple drug allergies or significant hypersensitivity may be at increased risk.

Due to overlap in signs and symptoms, it was not possible to distinguish between hypersensitivity reactions and infusion-related reactions in all cases. In the controlled clinical trials of BENLYSTA administered intravenously in adults with SLE, some subjects (13%) received premedication, which may have mitigated or masked a hypersensitivity response or infusion-related reaction; however, there is insufficient evidence to determine whether premedication diminishes the frequency or severity of hypersensitivity reactions or infusion-related reaction.

BENLYSTA for intravenous use should be administered by healthcare providers prepared to manage anaphylaxis and infusion-related reactions. Healthcare providers should be aware of the risk of hypersensitivity reactions, which may present as infusion-related reactions. In the event of a serious reaction, discontinue BENLYSTA immediately and administer appropriate medical therapy. With intravenous administration, the infusion rate may be slowed or interrupted if the patient develops an infusion reaction. Monitor patients during infusion and for an appropriate period of time after intravenous administration of BENLYSTA. Consider administering premedication as prophylaxis prior to intravenous dosing [see Dosage and Administration (2.1, 2.2)].

Inform patients receiving BENLYSTA of the signs and symptoms of hypersensitivity reactions and instruct them to seek immediate medical care should a reaction occur.

5.3 Depression and Suicidality

In controlled clinical trials, depression and suicidality were reported in subjects receiving BENLYSTA [see Adverse Reactions (6.1)]. Assess the risk of depression and suicide considering the patient’s medical history and current psychiatric status before treatment with BENLYSTA and continue to monitor patients during treatment. Instruct patients receiving BENLYSTA (and caregivers, if applicable) to contact their healthcare provider if they experience new or worsening depression, suicidal thoughts or behavior, or other mood changes. Consider the risk and benefit of continued treatment with BENLYSTA for patients who develop such symptoms.

5.4 Malignancy

There is an increased risk of malignancies with the use of immunosuppressants. The impact of treatment with BENLYSTA on the development of malignancies is not known [see Adverse Reactions (6.1)].

Consider the individual benefit-risk in patients with known risk factors for the development or reoccurrence of malignancy prior to prescribing BENLYSTA. In patients who develop malignancies, consider the risk and benefit of continued treatment with BENLYSTA.

5.5 Immunization

Because of its mechanism of action, BENLYSTA may interfere with the response to immunizations. Live vaccines should not be given for 30 days before or concurrently with BENLYSTA as clinical safety has not been established. No data are available on the secondary transmission of infection from persons receiving live vaccines to patients receiving BENLYSTA or the effect of BENLYSTA on new immunizations.

5.6 Concomitant Use with Other Biologic Therapies

Available data do not support the safety and efficacy of concomitant use of BENLYSTA with rituximab in patients with SLE. An increased incidence of serious infections and post-injection systemic reactions in subjects receiving BENLYSTA concomitantly with rituximab compared to subjects receiving BENLYSTA alone has been observed [see Adverse Reactions (6.1)]. The safety and efficacy of BENLYSTA concomitantly with other biologic therapies, including B-cell-targeted therapies, have not been established. Caution should be exercised if BENLYSTA is administered in combination with other biologic therapies [see Warnings and Precautions (5)].

6 ADVERSE REACTIONS

The following serious adverse reactions are described below and in the Warnings and Precautions section:

- Serious Infections [see Warnings and Precautions (5.1)]
- Hypersensitivity Reactions, including Anaphylaxis [see Warnings and Precautions (5.2)]
- Depression and Suicidality [see Warnings and Precautions (5.3)]
- Malignancy [see Warnings and Precautions (5.4)]

6.1 Clinical Trials Experience

Because clinical trials are conducted under widely varying conditions, adverse reaction rates observed in the clinical trials of a drug cannot be directly compared with rates in the clinical trials of another drug and may not reflect the rates observed in practice.

Intravenous Administration in Adult Subjects with Active SLE

The data described in Table 2 reflect exposure to BENLYSTA administered intravenously plus standard therapy compared with placebo plus standard therapy in 2,133 adult subjects with active SLE in 3 controlled trials (Trials 1, 2, and 3). Subjects received BENLYSTA plus standard therapy at doses of 1 mg/kg (n = 673), 4 mg/kg (n = 111; Trial 1 only), or 10 mg/kg (n = 674), or placebo plus standard therapy (n = 675) intravenously over a 1‑hour period on Days 0, 14, 28, and then every 28 days. In 2 of the trials (Trial 1 and Trial 3), treatment was given for 48 weeks, while in the other trial (Trial 2) treatment was given for 72 weeks [see Clinical Studies (14.2)]. Because there was no apparent dose‑related increase in the majority of adverse events observed with BENLYSTA, the safety data summarized below are presented for the 3 intravenous doses pooled, unless otherwise indicated; the adverse reaction table displays the results for the recommended intravenous dose of 10 mg/kg compared with placebo.

In Trials 1, 2, and 3, 93% of subjects treated with BENLYSTA plus standard therapy reported an adverse event compared with 92% treated with placebo plus standard therapy.

The most common serious adverse events were serious infections (6% and 5.2% in the groups receiving BENLYSTA and placebo plus standard therapy, respectively), some of which were fatal.

The most commonly reported adverse events, occurring in ≥5% of subjects in Trials 1, 2, and 3 were nausea, diarrhea, pyrexia, nasopharyngitis, bronchitis, insomnia, pain in extremity, depression, migraine, and pharyngitis.

The proportion of subjects who discontinued treatment due to any adverse reaction during Trials 1, 2, and 3 was 6.2% for subjects receiving BENLYSTA plus standard therapy and 7.1% for subjects receiving placebo plus standard therapy. The most common adverse reactions resulting in discontinuation of treatment (≥1% of subjects receiving BENLYSTA or placebo) were infusion reactions (1.6% BENLYSTA and 0.9% placebo), lupus nephritis (0.7% BENLYSTA and 1.2% placebo), and infections (0.7% BENLYSTA and 1% placebo).

Table 2 lists adverse reactions, regardless of causality, occurring in at least 3% of subjects with active SLE who received BENLYSTA 10 mg/kg plus standard therapy and at an incidence at least 1% greater than that observed with placebo plus standard therapy in 3 controlled trials (Trials 1, 2, and 3).

Table 2. Incidence of Adverse Reactions Occurring in at Least 3% of Adult Subjects with Active SLE Treated with BENLYSTA 10 mg/kg plus Standard Therapy and at Least 1% More Frequently than in Subjects Receiving Placebo plus Standard Therapy (Trials 1, 2, and 3)
Adverse Reactions | BENLYSTA; 10 mg/kg +; Standard Therapy; (n = 674); % | Placebo +; Standard Therapy; (n = 675); %
Nausea | 15 | 12
Diarrhea | 12 | 9
Pyrexia | 10 | 8
Nasopharyngitis | 9 | 7
Bronchitis | 9 | 5
Insomnia | 7 | 5
Pain in extremity | 6 | 4
Depression | 5 | 4
Migraine | 5 | 4
Pharyngitis | 5 | 3
Cystitis | 4 | 3
Leukopenia | 4 | 2
Gastroenteritis viral | 3 | 1

Specific Adverse Reactions in Adult Subjects with Active SLE (Intravenous Administration)

Infections: In Trials 1, 2, and 3, the overall incidence of infections was 71% in subjects receiving BENLYSTA compared with 67% in subjects receiving placebo. The most frequent infections (>5% of subjects receiving BENLYSTA) were upper respiratory tract infection, urinary tract infection, nasopharyngitis, sinusitis, bronchitis, and influenza. Infections leading to discontinuation of treatment occurred in 0.7% of subjects receiving BENLYSTA and 1.0% of subjects receiving placebo.

Serious Infections: In Trials 1, 2, and 3, the incidence of serious infections was 6.0% in subjects receiving BENLYSTA and 5.2% in subjects receiving placebo. The most frequent serious infections included pneumonia, urinary tract infections, cellulitis, and bronchitis. Fatal infections occurred in 0.3% (4/1,458) of subjects receiving BENLYSTA and in 0.1% (1/675) of subjects receiving placebo.

In a randomized, double‑blind, placebo‑controlled, 52‑week, postmarketing safety trial of BENLYSTA administered intravenously in adults with active SLE (N = 4,003), the incidence of serious infections was 3.7% in subjects receiving BENLYSTA compared with 4.1% in subjects receiving placebo. Serious infections leading to discontinuation of treatment occurred in 1.0% of subjects receiving BENLYSTA and in 0.9% of subjects receiving placebo. Fatal infections occurred in 0.45% (9/2,002) of subjects receiving BENLYSTA and in 0.15% (3/2,001) of subjects receiving placebo, where the incidence of all‑cause mortality was 0.50% (10/2,002) in subjects receiving BENLYSTA and 0.40% (8/2,001) in subjects receiving placebo.

Hypersensitivity Reactions, including Anaphylaxis: In Trials 1, 2, and 3, hypersensitivity reactions (occurring on the same day of infusion) were reported in 13% (191/1,458) of subjects receiving BENLYSTA and 11% (76/675) of subjects receiving placebo. Anaphylaxis was observed in 0.6% (9/1,458) of subjects receiving BENLYSTA and 0.4% (3/675) of subjects receiving placebo. Manifestations included hypotension, angioedema, urticaria or other rash, pruritus, and dyspnea.

Infusion‑Related Reactions: In Trials 1, 2, and 3, adverse events associated with the infusion (occurring on the same day of the infusion) were reported in 17% (251/1,458) of subjects receiving BENLYSTA and 15% (99/675) of subjects receiving placebo. Serious infusion reactions (excluding hypersensitivity reactions) were reported in 0.5% of subjects receiving BENLYSTA and 0.4% of subjects receiving placebo and included bradycardia, myalgia, headache, rash, urticaria, and hypotension. The most common infusion reactions (≥3% of subjects receiving BENLYSTA) were headache, nausea, and skin reactions.

Depression and Suicidality: In Trials 1, 2, and 3, psychiatric events were reported more frequently with BENLYSTA (16%) than with placebo (12%), primarily related to depression‑related events (6.3% BENLYSTA; 4.7% placebo), insomnia (6% BENLYSTA; 5.3% placebo), and anxiety (3.9% BENLYSTA; 2.8% placebo). Serious psychiatric events were reported in 0.8% (12/1,458) of subjects receiving BENLYSTA and 0.4% (3/675) of subjects receiving placebo. Serious depression was reported in 0.4% (6/1,458) of subjects receiving BENLYSTA and 0.1% (1/675) of subjects receiving placebo. Two suicides (0.1%) were reported in subjects receiving BENLYSTA (one with 10 mg/kg and one with 1 mg/kg).

In a 52‑week postmarketing safety trial of BENLYSTA (N = 4,003), serious psychiatric events were reported in 1% (20/2,002) of subjects receiving BENLYSTA and 0.3% (6/2,001) of subjects receiving placebo. Serious depression was reported in 0.3% (7/2,002) of subjects receiving BENLYSTA and in <0.1% (1/2,001) receiving placebo. The overall incidence of serious suicidal ideation or behavior or self‑injury without suicidal intent was 0.7% (15/2,002) of subjects receiving BENLYSTA and 0.2% (5/2,001) of subjects receiving placebo. On the Columbia‑Suicide Severity Rating Scale (C‑SSRS), 2.4% (48/1,974) of subjects receiving BENLYSTA reported suicidal ideation or behavior compared with 2% (39/1,988) of subjects receiving placebo. No suicide was reported in either group.

The intravenous trials above did not exclude subjects with a history of psychiatric disorders.

Malignancy: In Trials 1, 2, and 3, malignancies (including non‑melanoma skin cancers) were reported in 0.4% of subjects receiving BENLYSTA and 0.4% of subjects receiving placebo. In the intravenous controlled clinical trials, malignancies, excluding non‑melanoma skin cancers, were observed in 0.2% (3/1,458) and 0.3% (2/675) of subjects receiving BENLYSTA and placebo, respectively.

Intravenous Administration in Black/African‑American Subjects with Active SLE

The safety of BENLYSTA 10 mg/kg administered intravenously in adults plus standard therapy (n = 331) compared with placebo plus standard therapy (n = 165) in Black subjects with active SLE (Trial 4) was consistent with the known safety profile of BENLYSTA administered intravenously plus standard therapy in the overall population [see Clinical Studies (14.2)].

Intravenous Administration in Adult Subjects with Active Lupus Nephritis

The safety of BENLYSTA 10 mg/kg administered intravenously plus standard therapy (n = 224) compared with placebo plus standard therapy (n = 224) was evaluated in adults with active lupus nephritis for up to 104 weeks (Trial 5) [see Clinical Studies (14.3)]. The adverse reactions observed were consistent with the known safety profile of BENLYSTA administered intravenously plus standard therapy in patients with active SLE. Cases of myelosuppression, including febrile neutropenia, leukopenia, and pancytopenia, were observed in subjects who received induction therapy with cyclophosphamide followed by maintenance therapy with azathioprine, or mycophenolate.

Specific Adverse Reactions in Adult Subjects with Active Lupus Nephritis (Intravenous Administration)

Infections: In Trial 5, the overall incidence of infections was 82% in subjects receiving BENLYSTA compared with 76% in subjects receiving placebo.

Serious Infections: In Trial 5, serious infections occurred in 14% of subjects receiving BENLYSTA and in 17% of subjects receiving placebo. Fatal infections occurred in 0.9% (2/224) of subjects receiving BENLYSTA and in 0.9% (2/224) of subjects receiving placebo.

Intravenous Administration in Pediatric Subjects 5 Years of Age and Older with Active SLE

The safety of BENLYSTA administered intravenously plus standard therapy (n = 53) compared with placebo plus standard therapy (n = 40) was evaluated in 93 pediatric subjects with active SLE (Trial 6). The adverse reactions observed were consistent with those observed in adults with SLE [see Clinical Studies (14.4)].

Subcutaneous Administration in Adult Subjects with Active SLE

The data described below reflect exposure to BENLYSTA administered subcutaneously plus standard therapy compared with placebo plus standard therapy in 836 adult subjects with active SLE in a controlled trial (Trial 7). In addition to standard therapy, subjects received BENLYSTA 200 mg (n = 556) or placebo (n = 280) (2:1 randomization) once weekly for up to 52 weeks [see Clinical Studies (14.5)].

In the trial, 81% of subjects treated with BENLYSTA plus standard therapy reported an adverse event compared with 84% treated with placebo plus standard therapy. The proportion of subjects who discontinued treatment due to any adverse reaction during the controlled clinical trial was 7.2% of subjects receiving BENLYSTA plus standard therapy and 8.9% of subjects receiving placebo plus standard therapy.

The safety profile observed for BENLYSTA administered subcutaneously plus standard therapy was consistent with the known safety profile of BENLYSTA administered intravenously plus standard therapy, with the exception of local injection site reactions.

Infections: In Trial 7, the overall incidence of infections was 55% in subjects receiving BENLYSTA compared with 57% in subjects receiving placebo. The most commonly reported infections with BENLYSTA administered subcutaneously were similar to those reported with BENLYSTA administered intravenously.

Serious Infections: In Trial 7, the incidence of serious infections was 4.1% in subjects receiving BENLYSTA and 5.4% in subjects receiving placebo. Fatal infections occurred in 0.5% (3/556) of subjects receiving BENLYSTA and in none of the subjects receiving placebo (0/280).

Depression and Suicidality: In Trial 7, which excluded subjects with a history of psychiatric disorders, psychiatric events were reported in 6% of subjects receiving BENLYSTA and 11% of subjects receiving placebo. Depression‑related events were reported in 2.7% (15/556) of subjects receiving BENLYSTA and 3.6% (10/280) of subjects receiving placebo. Serious psychiatric events were reported in 0.2% (1/556) of subjects receiving BENLYSTA and in no subjects receiving placebo. There were no serious depression‑related events or suicides reported in either group. On the C‑SSRS, 1.3% (7/554) of subjects receiving BENLYSTA reported suicidal ideation or behavior compared with 0.7% (2/277) of subjects receiving placebo.

Malignancy: In Trial 7, the reports of malignancies were similar to those reported with BENLYSTA administered intravenously.

Injection Site Reactions: In Trial 7, the frequency of injection site reactions was 6.1% (34/556) for subjects receiving BENLYSTA plus standard therapy and 2.5% (7/280) for subjects receiving placebo plus standard therapy. These injection site reactions (most commonly pain, erythema, hematoma, pruritus, and induration) were mild to moderate in severity. The majority (94%) did not necessitate discontinuation of treatment.

Concomitant Use of Subcutaneous BENLYSTA and Intravenous Rituximab in Adult Subjects with Active SLE

BENLYSTA administered subcutaneously in combination with intravenous rituximab was studied in a Phase 3, randomized, double‑blind, placebo‑controlled, 104‑week trial in adult subjects with active SLE. Subjects were randomized to 1 of the 3 treatment arms: BENLYSTA with a single cycle of rituximab (n = 144); BENLYSTA with placebo (n = 72); BENLYSTA plus standard therapy (n = 76). In general, adverse reactions were consistent with the known safety profile of BENLYSTA and rituximab. When compared with BENLYSTA and placebo or BENLYSTA plus standard therapy, BENLYSTA in combination with rituximab was associated with higher frequency of serious adverse events (13.9%, 19.7%, 22.2%, respectively), serious infections (2.8%, 5.3%, 9.0%, respectively), and post‑injection systemic reactions (9.7%, 5.3%, 13.2%, respectively).

6.2 Postmarketing Experience

The following adverse reactions have been identified during post-approval use of BENLYSTA. Because these reactions are reported voluntarily from a population of uncertain size, it is not always possible to reliably estimate their frequency or establish a causal relationship to drug exposure.

- Fatal anaphylaxis [see Warnings and Precautions (5.2)].

7 DRUG INTERACTIONS

Formal drug interaction studies have not been performed with BENLYSTA. In clinical trials, BENLYSTA was administered concomitantly with other drugs, including corticosteroids, antimalarials, immunomodulatory and immunosuppressive agents (including azathioprine, cyclophosphamide, methotrexate, and mycophenolate), angiotensin pathway antihypertensives, HMG‑CoA reductase inhibitors (statins), and/or non-steroidal anti-inflammatory drugs (NSAIDs) without evidence of a clinically meaningful effect of these concomitant medications on belimumab pharmacokinetics. The effect of belimumab on the pharmacokinetics of other drugs has not been evaluated [see Clinical Pharmacology (12.3)].

8 USE IN SPECIFIC POPULATIONS

8.1 Pregnancy

Pregnancy Exposure Registry

There is a pregnancy exposure registry that evaluates pregnancy outcomes in women with lupus exposed to BENLYSTA during pregnancy. Healthcare professionals are encouraged to refer patients and pregnant women are encouraged to enroll themselves by calling 1-877-311-8972 or visiting https://mothertobaby.org/ongoing-study/benlysta-belimumab/.

Risk Summary

Available data on use of BENLYSTA in pregnant women, from observational studies, published case reports, and postmarketing surveillance, are insufficient to determine whether there is a drug-associated risk for major birth defects or miscarriage. There are risks to the mother and fetus associated with SLE (see Clinical Considerations). Monoclonal antibodies, such as belimumab, are actively transported across the placenta during the third trimester of pregnancy and may affect immune response in the in utero-exposed infant (see Clinical Considerations). In an animal combined embryo-fetal and pre- and post-natal development study with monkeys that received belimumab by intravenous administration, there was no evidence of fetal harm with exposures approximately 9 times (based on intravenous administration) and 20 times (based on subcutaneous administration) the exposure at the maximum recommended human dose (MRHD). Belimumab-related findings in monkey fetuses and/or infants included reductions of B-cell counts, reductions in the density of lymphoid tissue B-lymphocytes in the spleen and lymph nodes, and altered IgG and IgM titers. The no-adverse-effect-level (NOAEL) was not identified for these findings; however, they were reversible within 3 to 12 months after the drug was discontinued (see Data). Based on animal data and the mechanism of action of belimumab, the immune system in infants of treated mothers may be adversely affected. It is unknown, based on available data, whether immune effects, if identified, are reversible [see Clinical Pharmacology (12.1)].

The estimated background risk of major birth defects and miscarriage for the indicated population is unknown. All pregnancies have a background risk of birth defect, loss, or other adverse outcomes. In the U.S. general population, the background risk of major birth defects and miscarriage in clinically recognized pregnancies is 2% to 4% and 15% to 20%, respectively.

Clinical Considerations

Disease-Associated Maternal and/or Embryo/Fetal Risk: Pregnant women with SLE are at increased risk of adverse pregnancy outcomes, including worsening of the underlying disease, premature birth, miscarriage, and intrauterine growth restriction. Maternal lupus nephritis increases the risk of hypertension and preeclampsia/eclampsia. Passage of maternal autoantibodies across the placenta may result in adverse neonatal outcomes, including neonatal lupus and congenital heart block.

Fetal/Neonatal Adverse Reactions: Monoclonal antibodies are increasingly transported across the placenta as pregnancy progresses, with the largest amount transferred during the third trimester. Risks and benefits should be considered prior to administering live or live-attenuated vaccines to infants exposed to BENLYSTA in utero. Monitor an infant of a treated mother for B-cell reduction and other immune dysfunction [see Warnings and Precautions (5.5)].

Data

Animal Data: In a combined embryo-fetal and pre- and post-natal development study, pregnant cynomolgus monkeys received belimumab at intravenous doses of 0, 5, or 150 mg/kg every 2 weeks from confirmation of pregnancy at Gestation Days (GD) 20 to 22, throughout the period of organogenesis (up to approximately GD 50), and continuing to either the day of scheduled cesarean section (GD 150 [late third trimester]) or the day of parturition. There was no evidence of maternal toxicity, effects on embryofetal and infant survival, or structural abnormalities at exposure approximately 9 times the MRHD of 10 mg/kg intravenously or 20 times the MRHD of 200 mg subcutaneously (on an area under the curve [AUC] basis with maternal animal intravenous doses up to 150 mg/kg). Belimumab-related findings in mothers included reductions of immature and mature B-cell counts and in fetuses and/or infants included reductions of immature and mature B-cell counts, reductions in the density of lymphoid tissue B-lymphocytes in the spleen and lymph nodes, reduced spleen weights, increased IgG titers, and reduced IgM titers. B-cell counts in infant monkeys exposed to belimumab in utero recovered by 3 months of age and in mothers after 1 year. Immunoglobulin G (IgG) and IgM levels in infant monkeys recovered by 6 months of age and the reductions in B-lymphocytes in the lymph nodes and spleen were reversed by 1 year of age. Belimumab crossed the placenta, as it was detected in fetal cord blood and amniotic fluid on GD 150.

8.2 Lactation

Risk Summary

No information is available on the presence of belimumab in human milk, the effects of the drug on the breastfed infant, or the effects of the drug on milk production. Belimumab was detected in the milk of cynomolgus monkeys; however, due to species-specific differences in lactation physiology, animal data may not predict drug levels in human milk. Maternal IgG is known to be present in human milk. If belimumab is transferred into human milk, the effects of local exposure in the gastrointestinal tract and potential limited systemic exposure in the infant to belimumab are unknown. The lack of clinical data during lactation precludes clear determination of the risk of BENLYSTA to an infant during lactation; therefore, the developmental and health benefits of breastfeeding should be considered along with the mother’s clinical need for BENLYSTA, and any potential adverse effects on the breastfed child from BENLYSTA or from the underlying maternal condition.

8.3 Females and Males of Reproductive Potential

Contraception

Following an assessment of benefit versus risk, if prevention of pregnancy is warranted, females of reproductive potential should use effective contraception during treatment and for at least 4 months after the final treatment.

8.4 Pediatric Use

The safety and effectiveness of BENLYSTA have been established for the treatment of active SLE and active lupus nephritis in pediatric patients 5 years of age and older who are receiving standard therapy.

The safety and effectiveness of BENLYSTA have not been established in pediatric patients less than 5 years of age.

Intravenous Use

Use of BENLYSTA intravenously in pediatric patients 5 years of age and older with active SLE is supported by evidence from pharmacokinetic (PK), safety, and efficacy results from a pediatric trial (Trial 6), as well as PK exposure and extrapolation of the established efficacy of BENLYSTA plus standard therapy from the Phase 3 intravenous studies in adults with active SLE (Trials 2 and 3). In Trial 6, the proportion of pediatric subjects achieving an SRI‑4 response was higher in subjects receiving BENLYSTA plus standard therapy compared with placebo plus standard therapy. Pediatric subjects receiving BENLYSTA plus standard therapy also had a lower risk of experiencing a severe flare compared with placebo plus standard therapy [see Clinical Studies (14.4)]. Pharmacokinetics were evaluated in a total of 53 pediatric subjects (Trial 6) and were consistent with the adult population with active SLE [see Clinical Pharmacology (12.3)].

Use of BENLYSTA intravenously in pediatric patients 5 years of age and older with active lupus nephritis is based on the extrapolation of efficacy from the intravenous trial (Trial 5) in adults (n = 224) with active lupus nephritis, and supported by pharmacokinetic data from intravenous studies in adults (n = 224) with active lupus nephritis and from pediatric subjects (n = 53) with active SLE (Trial 6). Estimated belimumab exposures for pediatric patients were comparable to adults with active lupus nephritis [see Clinical Pharmacology (12.3)].

Subcutaneous Use

Use of BENLYSTA, administered subcutaneously in pediatric patients 5 years of age and older who weigh at least 15 kg with active SLE, is supported by evidence from an open‑label pharmacokinetic trial (subcutaneous administration of BENLYSTA in pediatric subjects with active SLE) and Trial 6 (a pharmacokinetic, efficacy, and safety trial of intravenous dosing in pediatric subjects with active SLE). The pharmacokinetics of belimumab, following subcutaneous administration in pediatric patients, are estimated to be comparable to adults who receive BENLYSTA subcutaneously and pediatric patients who receive BENLYSTA intravenously [see Clinical Pharmacology (12.3)].

Use of BENLYSTA, administered subcutaneously in pediatric patients 5 years of age and older who weigh at least 15 kg with active lupus nephritis, is based on the extrapolation of efficacy from the intravenous trial in adults (n = 224) with active lupus nephritis (Trial 5), and is supported by pharmacokinetic data derived from the same adult trial (Trial 5), a pharmacokinetic, efficacy, and safety intravenous trial in pediatric subjects with active SLE (n = 53) (Trial 6), and an open‑label subcutaneous trial in pediatric subjects with active SLE (n = 25). Belimumab exposures for pediatric patients with active lupus nephritis following subcutaneous administration are estimated to be comparable to adults with active lupus nephritis who receive BENLYSTA intravenously [see Clinical Pharmacology (12.3)].

8.5 Geriatric Use

Clinical studies of BENLYSTA did not include sufficient numbers of subjects, 65 years of age or older, to determine whether they respond differently from younger subjects. Use with caution in geriatric patients.

8.6 Renal Impairment

The safety and efficacy of BENLYSTA were evaluated in studies that included subjects with SLE who had mild (creatinine clearance [CrCl] ≥60 and <90 mL/min), moderate (CrCl ≥30 and <60 mL/min), or severe (CrCl ≥15 and <30 mL/min) renal impairment. No dosage adjustment is recommended in patients with renal impairment.

8.7 Hepatic Impairment

No formal trials were conducted to examine the effects of hepatic impairment on the pharmacokinetics of belimumab. No dosage adjustment is recommended in patients with hepatic impairment.

8.8 Racial Groups

In Trial 2 and Trial 3 (intravenous dosing), SLE Responder Index‑4 (SRI‑4) response rates were lower for Black subjects receiving BENLYSTA plus standard therapy relative to Black subjects receiving placebo plus standard therapy [see Clinical Studies (14.2)].

In Trial 4 (intravenous dosing), a 2:1 randomized, placebo‑controlled trial in Black subjects, SLE Responder Index (SRI‑S2K) response rates were higher for Black subjects receiving BENLYSTA plus standard therapy (49%) relative to Black subjects receiving placebo plus standard therapy (42%). However, the treatment difference was not statistically significant [see Clinical Studies (14.2)].

In Trial 7 (subcutaneous dosing), SRI‑4 response was 45% (26/58) in Black subjects receiving BENLYSTA plus standard therapy compared with 39% (13/33) in Black subjects receiving placebo plus standard therapy [see Clinical Studies (14.5)].

The safety profile of BENLYSTA in Black subjects was consistent with the known safety profile of BENLYSTA administered in the overall population [see Adverse Reactions (6.1)].

10 OVERDOSAGE

There is limited experience with overdosage of belimumab.

Two doses of up to 20 mg/kg have been given intravenously to humans with no increase in incidence or severity of adverse reactions compared with doses of 1, 4, or 10 mg/kg.

11 DESCRIPTION

Belimumab is a human IgG1λ monoclonal antibody specific for soluble human B lymphocyte stimulator protein (BLyS, also referred to as BAFF and TNFSF13B). Belimumab has a molecular weight of approximately 147 kDa. Belimumab is produced by recombinant DNA technology in a murine cell (NS0) expression system.

Intravenous Infusion

BENLYSTA (belimumab) for injection is a sterile, white to off-white, preservative‑free, lyophilized powder in a single-dose vial for reconstitution and dilution prior to intravenous infusion. BENLYSTA for injection is supplied as 120 mg per vial and 400 mg per vial and requires reconstitution with Sterile Water for Injection, USP (1.5 mL and 4.8 mL, respectively) to obtain a concentration of 80 mg/mL [see Dosage and Administration (2.2)]. After reconstitution, each vial allows for withdrawal of 1.5 mL (120 mg) or 5 mL (400 mg). Each mL delivers 80 mg belimumab, citric acid (0.16 mg), polysorbate 80 (0.4 mg), sodium citrate (2.7 mg), and sucrose (80 mg), with a pH of 6.5.

The vial stoppers are not made with natural rubber latex.

Subcutaneous Injection

BENLYSTA (belimumab) injection is a sterile, preservative-free, clear to opalescent, and colorless to pale yellow solution for subcutaneous use. It is supplied in a 1-mL single-dose prefilled autoinjector with a fixed 27-gauge, half-inch needle or in a 1-mL single-dose prefilled syringe with a fixed 27-gauge, half-inch needle with a needle guard. Each 1 mL delivers 200 mg belimumab, L-arginine hydrochloride (5.3 mg), L-histidine (0.65 mg), L-histidine monohydrochloride (1.2 mg), polysorbate 80 (0.1 mg), and sodium chloride (6.7 mg), with a pH of 6.0.

The autoinjectors and prefilled syringes are not made with natural rubber latex.

12 CLINICAL PHARMACOLOGY

12.1 Mechanism of Action

BENLYSTA is a BLyS-specific inhibitor that blocks the binding of soluble BLyS, a B-cell survival factor, to its receptors on B cells. BENLYSTA does not bind B cells directly, but by binding BLyS, BENLYSTA inhibits the survival of B cells, including autoreactive B cells, and reduces the differentiation of B cells into immunoglobulin-producing plasma cells.

12.2 Pharmacodynamics

Treatment with BENLYSTA in adult subjects significantly reduced circulating CD19+, CD20+, naïve, and activated B cells, and the SLE B‑cell subset at Week 52. Reductions in naïve and the SLE B‑cell subset were observed as early as Week 8 and sustained to Week 52. Memory cells increased initially and slowly declined toward baseline levels by Week 52.

Treatment with BENLYSTA in adult subjects led to reductions in IgG and anti‑double‑stranded DNA antibodies (anti‑dsDNA) which were observed as early as Week 8 and sustained through Week 52. In subjects with low complement levels at baseline, treatment led to increases in complement C3 and C4 as early as Week 12 and were sustained through Week 52.

The pharmacodynamic response observed in Black subjects (Trial 4) was consistent with the previous studies.

In subjects with active lupus nephritis (Trial 5), following treatment with BENLYSTA, there was a decrease in serum IgG as early as Week 4, and subsequently there was an increase in serum IgG levels which was associated with decreased proteinuria. Reductions in autoantibodies, increases in complement, and reductions in circulating total B cells and B‑cell subsets observed were consistent with the SLE studies.

In Trial 6 (pediatric dosing), the pharmacodynamic response was consistent with the adult data.

The clinical relevance of above mentioned pharmacodynamic biomarkers has not been established.

12.3 Pharmacokinetics

Intravenous Infusion in Adults

Systemic Lupus Erythematosus: The pharmacokinetic parameters displayed in Table 3 are based on population parameter estimates from 563 adult subjects with active SLE who received BENLYSTA 10 mg/kg.

Table 3. Population Pharmacokinetic Parameters in Adult Subjects with Active SLE after Intravenous Infusion of BENLYSTA 10 mg/kga
Pharmacokinetic Parameter | Population Estimates; (n = 563)
Peak concentration at steady state (Cmax,ss, mcg/mL) | 313
Area under the curve (AUC0-∞, day•mcg/mL) | 3,083
Distribution half-life (t½, days) | 1.8
Terminal half-life (t½, days) | 19.4
Systemic clearance (CL, mL/day) | 215
Volume of distribution at steady state (Vss, L) | 5
a Intravenous infusions were administered at 2‑week intervals for the first 3 doses and at 4‑week intervals thereafter.

Lupus Nephritis: A population pharmacokinetic analysis was conducted in 224 adult subjects with active lupus nephritis who received belimumab 10 mg/kg intravenously (Days 0, 14, 28, and then every 28 days up to 104 weeks) plus standard therapy in Trial 5 [see Clinical Studies (14.3)]. In these subjects, due to additional clearance associated with proteinuria, belimumab exposure was initially lower than observed in SLE studies and lower belimumab exposure was observed in subjects with higher proteinuria. When the proteinuria was decreased to approximately ≤1 g/g after treatment, belimumab clearance and exposure were similar to that observed in subjects with active SLE who received belimumab 10 mg/kg intravenously. The available data do not support a dose adjustment in patients with high proteinuria.

Subcutaneous Injection in Adults

Systemic Lupus Erythematosus: The pharmacokinetic parameters displayed in Table 4 are based on population parameter estimates from 661 adult subjects with active SLE after subcutaneous administration of belimumab 200 mg once weekly. The time to reach maximum serum concentration (Cmax) was 2.6 days (Tmax) after administration at steady state. The bioavailability of belimumab was approximately 74%. With weekly subcutaneous administration there were minor fluctuations around the steady‑state average concentration (Cavg,ss 104 mcg/mL), with the steady‑state trough concentration (Cmin,ss) (97 mcg/mL) being only slightly below Cavg,ss.

Table 4. Population Pharmacokinetic Parameters in Adults with Active SLE after Subcutaneous Administration of BENLYSTA 200 mg Once Weekly
Pharmacokinetic Parameter | Population Estimates; (n = 661)
Peak concentration at steady state (Cmax,ss, mcg/mL) | 108
Area under the curve (AUC0-∞, day•mcg/mL) | 726
Distribution half-life (t½, days) | 1.1
Terminal half-life (t½, days) | 18.3
Systemic clearance (CL, mL/day) | 204
Volume of distribution at steady state (Vss, L) | 5

Lupus Nephritis: Based on population pharmacokinetic modeling and simulation of the subcutaneous 400-mg weekly loading dose, the average belimumab concentration during the first 12 weeks was predicted to be 78 mcg/mL, which is similar to the estimated concentration of 89 mcg/mL for intravenous administration. The loading dose of 400 mg weekly provides steady-state concentrations from Week 2 of dosing. The steady-state average concentrations of subcutaneous administration of belimumab 200 mg once weekly in adults with active lupus nephritis are predicted to be similar to those observed in adults with active lupus nephritis receiving belimumab 10 mg/kg intravenously every 4 weeks.

Specific Populations

The following information is based on the population pharmacokinetic analyses of intravenous administration and subcutaneous administration of BENLYSTA.

Age: Age did not significantly influence the pharmacokinetics of belimumab, where the majority of subjects were between 18 and 45 years of age (70% with intravenous dosing; 74% with subcutaneous dosing).

Geriatric Patients: Limited pharmacokinetic data are available for elderly patients as less than 2% of the subjects included in the pharmacokinetic analysis were 65 years of age or older [see Use in Specific Populations (8.5)].

Pediatric Patients:

- Intravenous Administration in Pediatric Patients with Active SLE: The pharmacokinetic parameters of belimumab after intravenous administration in pediatric subjects with active SLE are based on individual parameter estimates from a population pharmacokinetic analysis of 53 pediatric subjects with active SLE (Trial 6). Following intravenous administration of 10 mg/kg on Days 0, 14, and 28, and at 4‑week intervals thereafter, belimumab exposures were similar between pediatric and adult subjects with active SLE. Steady‑state geometric mean Cmax, Cmin, Cavg, and AUC values were 305, 42, 92 mcg/mL, and 2,569 day•mcg/mL in the 5‑year to 11‑year‑old group, and 317, 52, 112 mcg/mL and 3,126 day•mcg/mL in the 12‑year to 17‑year‑old group [see Use in Specific Populations (8.4)].
- Subcutaneous Administration in Pediatric Patients with Active SLE: The pharmacokinetic parameters of belimumab, following subcutaneous administration in pediatric subjects with active SLE, are based on a population pharmacokinetic analysis derived from 25 pediatric subjects with active SLE who received BENLYSTA subcutaneously and Trial 6 (a Phase 2 trial in pediatric subjects with active SLE receiving BENLYSTA intravenously). Following subcutaneous administration of 200 mg of BENLYSTA in pediatric subjects 5 years to less than 18 years of age, either weekly (subjects weighing greater than or equal to 40 kg) or every 2 weeks (subjects weighing 15 to less than 40 kg), the steady state average belimumab concentration is estimated to be similar to that of adult subjects with active SLE following subcutaneous administration of BENLYSTA 200 mg weekly and similar to that of pediatric subjects with active SLE following intravenous administration of 10 mg/kg BENLYSTA on Days 0, 14, and 28, and at 4‑week intervals thereafter. Simulated steady‑state geometric mean Cmax and AUC are estimated to be 110 mcg/mL and 1,328 day•mcg/mL for pediatric subjects (weighing 15 to less than 40 kg) receiving BENLYSTA 200 mg every 2 weeks, and 134 mcg/mL and 899 day•mcg/mL for pediatric subjects (weighing greater than or equal to 40 kg) receiving BENLYSTA 200 mg once weekly [see Use in Specific Populations (8.4)].
- Intravenous Administration in Pediatric Patients with Active Lupus Nephritis: The pharmacokinetics of belimumab, following intravenous administration in pediatric patients with active lupus nephritis, were estimated based on a population pharmacokinetic model developed from intravenous pharmacokinetics data from 224 adults with active lupus nephritis in Trial 5 and validated using intravenous pharmacokinetics data from 53 pediatric subjects with active SLE in Trial 6. Based on modeling and simulation results, with intravenous administration of 10 mg/kg on Days 0, 14, and 28 and at 4‑week intervals thereafter, the simulated belimumab exposures for both the 5‑year to 11‑year‑old group and the 12‑year to 17‑year‑old group of pediatric subjects were estimated to be comparable to adults with active lupus nephritis [see Use in Specific Populations (8.4)].
- Subcutaneous Administration in Pediatric Patients with Active Lupus Nephritis: The pharmacokinetics of belimumab, following subcutaneous administration in pediatric patients with active lupus nephritis, were extrapolated from previously developed pediatric and adult pharmacokinetic models (Trials 5 and 6) and validated using data from pediatric subjects with active SLE who received BENLYSTA intravenously (Trial 6) and subcutaneously. Based on the modeling and simulation results, following subcutaneous administration of BENLYSTA in pediatric subjects with active lupus nephritis aged 5 years to less than 18 years, receiving either 400 mg once weekly for 4 doses, then 200 mg every week thereafter (subjects weighing greater than or equal to 40 kg) or 200 mg once weekly for 4 doses then 200 mg once every 2 weeks (subjects weighing 15 to less than 40 kg), the simulated belimumab exposures were estimated to be comparable to that of adults with active lupus nephritis [see Use in Specific Populations (8.4)].

Male and Female Patients: Gender did not significantly influence belimumab pharmacokinetics in the largely female trial population (94% with intravenous dosing; 85% with subcutaneous dosing).

Racial Groups: Race did not significantly influence belimumab pharmacokinetics. The racial distribution with intravenous administration was 53% White, 16% Asian, 16% Alaska native/American Indian, and 14% Black in Trials 1, 2, and 3. Trial 4 enrolled only Black subjects. The racial distribution with subcutaneous administration (Trial 7) was 61% White, 20% Asian, 11% Black, and 6% Alaska native/American Indian.

Weight: Body weight and body mass index (BMI) had no clinically relevant effect on the pharmacokinetics of belimumab administered subcutaneously in adults. No dose adjustment is recommended in adults based on weight or BMI for subcutaneous administration.

The effects of body weight on belimumab exposure, after subcutaneous administration in pediatric patients, have been determined using a population pharmacokinetic model. Pediatric patients with lower body weight have lower belimumab clearance and volume of distribution. To ensure belimumab exposures remain within acceptable limits and are consistent across the pediatric weight range, patients with lower body weight are given a lower dose of BENLYSTA or administered BENLYSTA less frequently [see Dosage and Administration (2.3)].

Patients with Renal Impairment: No formal trials were conducted to examine the effects of renal impairment on the pharmacokinetics of belimumab. BENLYSTA was studied in a limited number of adult subjects with SLE who had mild (CrCl ≥60 and <90 mL/min), moderate (CrCl ≥30 and <60 mL/min), or severe (CrCl ≥15 and <30 mL/min) renal impairment: 770 subjects with mild renal impairment, 261 subjects with moderate renal impairment, and 14 subjects with severe renal impairment received belimumab intravenously; 121 subjects with mild renal impairment and 30 subjects with moderate renal impairment received belimumab subcutaneously [see Use in Specific Populations (8.6)].

Patients with Hepatic Impairment: No formal trials were conducted to examine the effects of hepatic impairment on the pharmacokinetics of belimumab. Baseline alanine aminotransferase (ALT) and aspartate aminotransferase (AST) levels did not significantly influence belimumab pharmacokinetics [see Use in Specific Populations (8.7)].

Drug Interaction Studies

No formal drug interaction studies have been conducted with BENLYSTA. Concomitant use of mycophenolate, cyclophosphamide, azathioprine, methotrexate, antimalarials, NSAIDs, aspirin, and/or HMG‑CoA reductase inhibitors did not significantly influence belimumab pharmacokinetics. Coadministration of steroids and angiotensin‑converting enzyme (ACE) inhibitors resulted in an increase of systemic clearance of belimumab that was not clinically significant because the magnitude was well within the range of normal variability of clearance. The effect of belimumab on the pharmacokinetics of other drugs has not been evaluated.

12.6 Immunogenicity

The observed incidence of anti‑drug antibodies is highly dependent on the sensitivity and specificity of the assay. Differences in assay methods preclude meaningful comparisons of the incidence of anti-drug antibodies in the studies described below with the incidence of anti‑drug antibodies in other studies, including those of BENLYSTA or of other belimumab products.

In Trials 2 and 3 (intravenous dosing in adults with active SLE), anti‑belimumab antibodies were assessed during the respective 52‑week and 76‑week, placebo‑controlled periods and detected in 4 of 563 (0.7%) subjects receiving BENLYSTA 10 mg/kg and in 27 of 559 (4.8%) subjects receiving BENLYSTA 1 mg/kg. The reported frequency for the group receiving 10 mg/kg may underestimate the actual frequency due to lower assay sensitivity in the presence of high drug concentrations. Neutralizing antibodies were detected in 3 subjects receiving BENLYSTA 1 mg/kg. Three subjects with anti‑belimumab antibodies experienced mild infusion reactions of nausea, erythematous rash, pruritus, eyelid edema, headache, and dyspnea; none of the reactions were life‑threatening. In Trial 4 (intravenous dosing in adult Black subjects), anti‑belimumab antibodies were detected in 2 of 321 (0.6%) subjects receiving BENLYSTA 10 mg/kg during the 52‑week, placebo‑controlled period. In Trial 5 (intravenous dosing in adults with active lupus nephritis), there was no formation of anti‑belimumab antibodies in 224 subjects receiving BENLYSTA 10 mg/kg plus standard therapy during the 104‑week, placebo‑controlled period. In Trial 6 (intravenous dosing in pediatric subjects with active SLE), there was no formation of anti‑belimumab antibodies in 53 subjects receiving BENLYSTA 10 mg/kg plus standard therapy during the 52‑week, placebo‑controlled period. In Trial 7 (subcutaneous dosing in adults with active SLE), there was no formation of anti‑belimumab antibodies in 556 subjects receiving BENLYSTA 200 mg during the 52‑week, placebo‑controlled period. In a 52‑week, open‑label, pediatric pharmacokinetic trial (subcutaneous dosing in pediatric subjects with active SLE), none of the 25 subjects developed anti‑belimumab antibodies.

The clinical relevance of the presence of anti‑belimumab antibodies is not known.

13 NONCLINICAL TOXICOLOGY

13.1 Carcinogenesis, Mutagenesis, Impairment of Fertility

Long-term animal studies have not been performed to evaluate the carcinogenic potential of belimumab.

Effects on male and female fertility have not been directly evaluated in animal studies.

14 CLINICAL STUDIES

14.1 Overview of Clinical Trials

The safety and effectiveness of BENLYSTA administered:

- Intravenously plus standard therapy were evaluated in 4 randomized, double‑blind, placebo‑controlled trials with 2,581 adult subjects with active SLE (Trial 1, NCT00071487, Trial 2, NCT00410384, Trial 3, NCT00424476, and Trial 4 NCT01632241) [see Clinical Studies (14.2)], and one randomized, double‑blind, placebo‑controlled trial with 93 pediatric subjects 5 years of age and older with active SLE (Trial 6, NCT01649765) [see Clinical Studies (14.4)], according to the American College of Rheumatology criteria. In these trials, subjects with severe active lupus nephritis and severe active CNS lupus were excluded. Subjects were on a stable standard therapy SLE treatment regimen comprising any of the following (alone or in combination): corticosteroids, antimalarials, NSAIDs, and immunosuppressives. Use of other biologics and intravenous cyclophosphamide was not permitted.
- Intravenously plus standard therapy were evaluated in a randomized, double‑blind, placebo‑controlled trial in 448 adult subjects with active lupus nephritis (Trial 5; NCT01639339) [see Clinical Studies (14.3)].
- Subcutaneously plus standard therapy in adults were evaluated in a randomized, double‑blind, placebo‑controlled trial in 836 adult subjects with active SLE (Trial 7; NCT01484496) [see Clinical Studies (14.5)].

14.2 Intravenous Administration in Adults with Active SLE

Trial 1: Active SLE – BENLYSTA 1 mg/kg, 4 mg/kg, 10 mg/kg - Intravenous

Trial 1 enrolled 449 adult subjects and evaluated doses of 1, 4, and 10 mg/kg BENLYSTA plus standard therapy compared with placebo plus standard therapy over 52 weeks in subjects with SLE. Subjects had to have a Safety of Estrogens in Lupus Erythematosus National Assessment‑Systemic Lupus Erythematosus Disease Activity Index (SELENA‑SLEDAI) score of ≥4 at baseline and a history of autoantibodies (anti‑nuclear antibody [ANA] and/or anti–double‑stranded DNA [anti‑dsDNA]), but 28% of the population was autoantibody negative at baseline. The co-primary endpoints were percent change in SELENA-SLEDAI score at Week 24 and time to first flare over 52 weeks. No significant differences between any of the groups receiving BENLYSTA and the group receiving placebo were observed. Exploratory analysis of this trial identified a subgroup of subjects (72%) who were autoantibody positive in whom BENLYSTA appeared to offer benefit. The results of this trial informed the design of Trials 2 and 3 and led to the selection of a target population limited to autoantibody‑positive SLE patients.

Trials 2, 3, and 4: Active SLE – BENLYSTA 1 mg/kg and 10 mg/kg - Intravenous

Trials 2 and 3 were randomized, double‑blind, placebo‑controlled trials in adult subjects with SLE that were similar in design except duration; Trial 2 (N = 819) was 76 weeks’ duration and Trial 3 (N = 865) was 52 weeks’ duration. Subjects had active SLE disease with a SELENA‑SLEDAI score ≥6 and positive autoantibody test results at screening. Subjects were excluded from the trial if they had ever received treatment with a B‑cell–targeted agent or if they were currently receiving other biologic agents. Intravenous cyclophosphamide was not permitted within the previous 6 months or during the trial. Trial 2 was conducted primarily in North America and Europe. Trial 3 was conducted in South America, Eastern Europe, Asia, and Australia.

Baseline concomitant medications included corticosteroids (Trial 2: 76%, Trial 3: 96%), immunosuppressives (Trial 2: 56%, Trial 3: 42%; including azathioprine, methotrexate, and mycophenolate), and antimalarials (Trial 2: 63%, Trial 3: 67%). Most subjects (>70%) were receiving 2 or more classes of SLE medications.

In Trial 2 and Trial 3, more than 50% of subjects had 3 or more active organ systems involved at baseline. The most common active organ systems at baseline based on SELENA‑SLEDAI were mucocutaneous (82% in both trials), immune (Trial 2: 74%, Trial 3: 85%), and musculoskeletal (Trial 2: 73%, Trial 3: 59%). Less than 16% of subjects had some degree of renal activity and less than 7% of subjects had activity in the vascular, cardio‑respiratory, or CNS systems.

At screening, subjects were stratified by disease severity based on their SELENA‑SLEDAI score (≤9 vs. ≥10), proteinuria level (<2 g/24 h vs. ≥2 g/24 h), and race (African or Indigenous‑American descent vs. other), and then randomly assigned to receive BENLYSTA 1 mg/kg, BENLYSTA 10 mg/kg, or placebo in addition to standard therapy. The subjects were administered trial medication intravenously over a 1‑hour period on Days 0, 14, 28, and then every 28 days for 48 weeks in Trial 3 and for 72 weeks in Trial 2.

The primary efficacy endpoint was a composite endpoint (SLE Responder Index‑4 or SRI‑4) that defined response as meeting each of the following criteria at Week 52 compared with baseline:

- ≥4‑point reduction in the SELENA‑SLEDAI score, and
- no new British Isles Lupus Assessment Group (BILAG) A organ domain score or 2 new BILAG B organ domain scores, and
- no worsening (<0.30‑point increase) in Physician’s Global Assessment (PGA) score.

The SRI uses the SELENA‑SLEDAI score as an objective measure of reduction in global disease activity; the BILAG index to ensure no significant worsening in any specific organ system; and the PGA to ensure that improvements in disease activity are not accompanied by worsening of the patient’s condition overall.

In both Trials 2 and 3, the proportion of subjects with SLE achieving an SRI‑4 response, as defined for the primary endpoint, was significantly higher in the group receiving BENLYSTA 10 mg/kg plus standard therapy than in the group receiving placebo plus standard therapy. The effect on the SRI-4 was not consistently significantly different for subjects receiving BENLYSTA 1 mg/kg plus standard therapy relative to placebo plus standard therapy in both trials. The 1‑mg/kg dose is not recommended. The trends in comparisons between the treatment groups for the rates of response for the individual components of the endpoint were generally consistent with that of the SRI‑4 (Table 5). At Week 76 in Trial 2, the SRI‑4 response rate with BENLYSTA 10 mg/kg was not significantly different from that of placebo (39% and 32%, respectively).

Table 5. Clinical Response Rate in Adult Subjects with Active SLE after 52 Weeks of Intravenous Treatment (Trials 2 and 3)
Response | Trial 2 |  |  | Trial 3
Response | Placebo + Standard Therapy; (n = 275) | BENLYSTA; 1 mg/kg + Standard Therapya; (n = 271) | BENLYSTA; 10 mg/kg + Standard Therapy; (n = 273) | Placebo + Standard Therapy; (n = 287) | BENLYSTA; 1 mg/kg + Standard Therapya; (n = 288) | BENLYSTA; 10 mg/kg + Standard Therapy; (n = 290)
SLE Responder Index-4 (SRI-4)b | 34% | 41% P = 0.104 | 43% P = 0.021 | 44% | 51% P = 0.013 | 58% P <0.001
Odds Ratio; (95% CI) vs. placebo |  | 1.3; (0.9, 1.9) | 1.5; (1.1, 2.2) |  | 1.6; (1.1, 2.2) | 1.8; (1.3, 2.6)
Components of SLE Responder Index-4 (SRI-4)
Percent of subjects with reduction in SELENA-SLEDAI ≥4 | 36% | 43% | 47% | 46% | 53% | 58%
Percent of subjects with no worsening by BILAG index | 65% | 75% | 69% | 73% | 79% | 81%
Percent of subjects with no worsening by PGA | 63% | 73% | 69% | 69% | 79% | 80%
a The 1-mg/kg dose is not recommended.
b Subjects dropping out of the trial early or experiencing certain increases in background medication were considered as failures in these analyses. In both trials, a higher proportion of placebo subjects were considered as failures for this reason compared with the groups receiving BENLYSTA.

The reduction in disease activity seen in the SRI-4 was related primarily to improvement in the most commonly involved organ systems; namely, mucocutaneous, musculoskeletal, and immune.

Effect in Black/African-American Subjects: In Trials 2 and 3, exploratory sub‑group analyses of SRI-4 response rate in Black subjects (n = 148) were performed. The SRI‑4 response rate in Black subjects in groups receiving BENLYSTA plus standard therapy was less than that in the group receiving placebo plus standard therapy (22/50 or 44% for placebo, 15/48 or 31% for BENLYSTA 1 mg/kg, and 18/50 or 36% for BENLYSTA 10 mg/kg).

Trial 4 included 448 Black subjects and was conducted in North America, South America, Europe, and Africa. It had the same trial design as Trials 2 and 3 with exceptions of subjects having a baseline SELENA‑SLEDAI score of ≥8 and using the modified SLEDAI‑2K scoring for proteinuria. The population had a mean age of 39 years (range: 18 to 71) and 97% were female. The proportion of Black subjects achieving an SRI‑S2K response at Week 52 (primary endpoint), and the individual components of the endpoint, were higher in the group receiving BENLYSTA 10 mg/kg plus standard therapy relative to the group receiving placebo plus standard therapy. However, the treatment difference was not statistically significant (Table 6).

Table 6. Clinical Response Rate in Black Adult Subjects with Active SLE after 52 Weeks of Intravenous Treatment (Trial 4)
Responsea | Placebo +; Standard Therapy; (n = 149) | BENLYSTA; 10 mg/kg +; Standard Therapy; (n = 298)
SLE Responder Index (SRI-S2K)b | 42% | 49%
Odds Ratio (95% CI) vs. placebo |  | 1.4 (0.9, 2.1); P = 0.107
Components of SLE Responder Index (SRI-S2K)
Percent of subjects with reduction in SELENA‑SLEDAI-S2K ≥4 | 42% | 50%
Odds Ratio (95% CI) vs. placebo |  | 1.5 (1.0, 2.2)
Percent of subjects with no worsening by BILAG index | 62% | 68%
Odds Ratio (95% CI) vs. placebo |  | 1.2 (0.8, 1.9)
Percent of subjects with no worsening by PGA | 64% | 70%
Odds Ratio (95% CI) vs. placebo |  | 1.3 (0.8, 1.9)
a Analyses excluded any subject missing a baseline assessment for any of the components (1 for belimumab).
b Subjects dropping out of the trial early or experiencing certain increases in background medication were considered as failures in these analyses. A higher proportion of subjects receiving placebo were considered as failures for this reason compared with the group receiving BENLYSTA.

Effect on Concomitant Steroid Treatment: In Trial 2 and Trial 3, 46% and 69% of subjects, respectively, were receiving prednisone at doses >7.5 mg/day at baseline. The proportion of subjects able to reduce their average prednisone dose by at least 25% to ≤7.5 mg/day during Weeks 40 through 52 was not consistently significantly different for BENLYSTA plus standard therapy relative to placebo plus standard therapy in both trials. In Trial 2, 17% of subjects receiving BENLYSTA 10 mg/kg plus standard therapy and 19% of subjects receiving BENLYSTA 1 mg/kg plus standard therapy achieved this level of steroid reduction compared with 13% of subjects receiving placebo plus standard therapy. In Trial 3, 19%, 21%, and 12% of subjects receiving BENLYSTA 10 mg/kg, BENLYSTA 1 mg/kg, and placebo, respectively, plus standard therapy achieved this level of steroid reduction.

Effect on Severe SLE Flares: The probability of experiencing a severe SLE flare, as defined by a modification of the SELENA Trial flare criteria, which excluded severe flares triggered only by an increase of the SELENA‑SLEDAI score to >12, was calculated for both Trials 2 and 3. The proportion of subjects having at least 1 severe flare over 52 weeks was not consistently significantly different for BENLYSTA plus standard therapy relative to placebo plus standard therapy in both trials. In Trial 2, 18% of subjects receiving BENLYSTA 10 mg/kg plus standard therapy and 16% of subjects receiving BENLYSTA 1 mg/kg plus standard therapy had a severe flare compared with 24% of subjects receiving placebo plus standard therapy. In Trial 3, 14%, 18%, and 23% of subjects receiving BENLYSTA 10 mg/kg, BENLYSTA 1 mg/kg and placebo, respectively, plus standard therapy had a severe flare.

14.3 Intravenous Administration in Adults with Active Lupus Nephritis

Trial 5: Active Lupus Nephritis – BENLYSTA 10 mg/kg - Intravenous

The safety and effectiveness of BENLYSTA 10 mg/kg administered intravenously over 1 hour on Days 0, 14, 28, and then every 28 days plus standard therapy were evaluated in a 104‑week, randomized, double‑blind, placebo‑controlled trial in 448 adult subjects with active proliferative and/or membranous lupus nephritis (Trial 5). The subjects had a clinical diagnosis of SLE according to American College of Rheumatology classification criteria; biopsy‑proven lupus nephritis Class III, IV, and/or V; and had active renal disease at screening requiring standard therapy: corticosteroids with 1) mycophenolate for induction followed by mycophenolate for maintenance, or 2) cyclophosphamide for induction followed by azathioprine for maintenance. This trial was conducted in Asia, North America, South America, and Europe. The mean age of subjects was 33 years (range: 18 to 77); the majority (88%) were female.

The primary efficacy endpoint was Primary Efficacy Renal Response (PERR) at Week 104, defined as a response at Week 100 confirmed by a repeat measurement at Week 104 of the following parameters: urine protein:creatinine ratio (uPCR) ≤0.7 g/g and estimated glomerular filtration rate (eGFR) ≥60 mL/min/1.73 m^2 or no decrease in eGFR of >20% from pre‑flare value.

The major secondary endpoints included:

- Complete Renal Response (CRR) defined as a response at Week 100 confirmed by a repeat measurement at Week 104 of the following parameters: uPCR <0.5 g/g and eGFR ≥90 mL/min/1.73 m^2 or no decrease in eGFR of >10% from pre-flare value.
- PERR at Week 52.
- Time to renal-related event or death (renal-related event defined as first event of end-stage renal disease, doubling of serum creatinine, renal worsening [defined by quantified increase in proteinuria and/or impaired renal function], or receipt of renal disease-related prohibited therapy due to inadequate lupus nephritis control or renal flare management).

The proportion of subjects achieving PERR at Week 104 was significantly higher in subjects receiving BENLYSTA plus standard therapy compared with placebo plus standard therapy (Table 7). The major secondary endpoints also showed significant improvement with BENLYSTA plus standard therapy compared with placebo plus standard therapy (Table 7 and Table 8).

Table 7. Efficacy Results in Adult Subjects with Active Lupus Nephritis (Intravenous Treatment) (Trial 5)
Efficacy Endpointa | Placebo + Standard Therapy n = 223 | BENLYSTA + Standard Therapy n = 223 | Odds Ratio (OR) vs. Placebo (95% CI)
Primary Efficacy Renal Response (PERR) at Week 104b,c (responders) | 32% | 43% | 1.6; (1.0, 2.3); P = 0.031
Components of PERR
Urine protein:creatinine ratio ≤0.7 g/g | 34% | 44% | 1.5; (1.0, 2.3)
eGFR ≥60 mL/min/1.73 m^2 or no decrease in eGFR from pre-flare value of >20% | 50% | 57% | 1.3; (0.9, 1.9)
Complete Renal Response (CRR) at Week 104b,c (responders) | 20% | 30% | 1.7; (1.1, 2.7); P = 0.017
Components of CRR
Urine protein:creatinine ratio <0.5 g/g | 29% | 39% | 1.6; (1.1, 2.4)
eGFR ≥90 mL/min/1.73 m^2 or no decrease in eGFR from pre-flare value of >10% | 40% | 47% | 1.3; (0.9, 2.0)
PERR at Week 52b (responders) | 35% | 47% | 1.6; (1.1, 2.4); P = 0.025
eGFR = Estimated glomerular filtration rate.
a PERR at Week 104 was the primary efficacy analysis; CRR at Week 104 and PERR at Week 52 were included in pre-specified testing hierarchy.
b In order to be considered a responder, steroid treatment had to be reduced to ≤10 mg/day from Week 24. Subjects who discontinued treatment early, received prohibited medication or increases in background standard therapy, or withdrew from the trial were considered non-responders. Prohibited medications and increases in background standard therapy were defined as: 1) use of corticosteroids above that allowed by protocol; 2) additional immunosuppressive agents (except topicals) beyond their induction/maintenance regimens; 3) angiotensin converting enzyme inhibitors (ACE) inhibitors, angiotensin II receptor blockers (ARBs), or antimalarials initiated after Week 24; 4) exceeding protocol-permitted doses for standard therapy (cyclophosphamide, azathioprine, mycophenolate); or 5) other biologics, intravenous immunoglobulin (IVIG), or plasmapheresis.
c The percentage of subjects who did not take prohibited medications or have an increase in background standard therapy at Week 104 was 83% for BENLYSTA and 74% for placebo.

In descriptive subgroup analyses, the PERR and CRR rates were examined by induction therapy (mycophenolate or cyclophosphamide), biopsy class (Class III or IV, Class III + V or Class IV + V, or Class V), and uPCR levels at baseline (<3 g/g or ≥3 g/g; post-hoc analysis) (Figure 1).

Figure 1. Odds Ratio of PERR and CRR at Week 104 across Subgroupsa, b in Adult Subjects with Active Lupus Nephritis (Intravenous Treatment) (Trial 5)

a Class III = Focal proliferative lupus nephritis; Class IV = Diffuse proliferative lupus nephritis; Class V = Membranous lupus nephritis; Class III + V = Mixed membranous-focal proliferative lupus nephritis; Class IV + V = Mixed membranous-diffuse proliferative lupus nephritis.

b Baseline urine protein:creatinine ratio (uPCR) was a post-hoc analysis.

The proportion of responders for PERR by visit through Week 104 is shown in Figure 2.

Figure 2. Primary Efficacy Renal Response (PERR) in Adult Subjects with Active Lupus Nephritis (+/- Standard Error) by Visita (Intravenous Treatment) (Trial 5)

a Analysis is descriptive; bars represent standard error. The same subjects may not have responded at each timepoint.

In Trial 5, subjects who received BENLYSTA were significantly less likely to experience a renal-related event or death compared with placebo (Table 8).

Table 8. Time to RenalRelated Event or Deatha in Adult Subjects with Active Lupus Nephritis (Intravenous Treatment) (Trial 5)
 | Placebo + Standard Therapy n = 223 | BENLYSTA + Standard Therapy n = 223 | Hazard Ratio (HR) vs. Placebo (95% CI)
Percentage (Number) of subjects with eventb | 28% (63) | 16% (35)
Time to eventc |  |  | 0.5; (0.3, 0.8); P = 0.001
Components of endpointd
(percentage of subjects with event)
End-stage renal disease (ESRD) | 0.4% | 1%
Doubling of serum creatinine from baseline | 4% | 1%
Renal worseninge | 18% | 8%
Renal-related treatment failuref | 16% | 9%
Death | 1% | 0.4%
a Time to renal-related event or death included in pre-specified testing hierarchy.
b When excluding deaths from analysis (1 for BENLYSTA; 2 for placebo), the percentage of subjects with a renal-related event was 15% for BENLYSTA compared with 27% for placebo (HR = 0.5; 95% CI: 0.3, 0.8).
c Subjects who discontinued treatment, were withdrawn from the trial, lost to follow-up, or had a treatment failure not related to renal disease were censored on the date of the event. Subjects who completed the 104-week treatment period were censored at the Week 104 visit. Time to event was defined as (event date minus treatment start date plus 1 day).
d Subjects could have had more than one event; the first event contributed to the overall endpoint.
e Renal worsening was prospectively defined as the development of increased proteinuria and/or impaired renal function defined as: 1) Increased proteinuria (using spot urine): a reproducible increase in 24-hour urine protein levels to >1 g/g if the baseline value was <0.2 g/g or >2 g/g if the baseline value was between 0.2 g/g and 1 g/g or more than twice the value at baseline if the baseline value was >1 g/g; and 2) Impaired renal function: a reproducible decrease in eGFR of >20% accompanied by at least 1 of the following: proteinuria (>1 g/g), red blood cell casts, or white blood cell casts.
f Renal-related treatment failure was prospectively defined as intake of prohibited medications for adjudicated inadequate lupus nephritis control or renal flare management.

In descriptive subgroup analyses of time to renal-related event or death, results were consistent with the overall endpoint regardless of induction therapy (mycophenolate or cyclophosphamide), biopsy class (Class III or IV, Class III + V or Class IV + V, or Class V; post-hoc analysis), and baseline proteinuria (<3 g/g or ≥3 g/g; post-hoc analysis). The treatment difference was primarily driven by the renal worsening and renal-related treatment failure components of the endpoint.

14.4 Intravenous Administration in Pediatric Subjects with Active SLE

Trial 6: Active SLE - BENLYSTA 10 mg/kg in Pediatric Subjects - Intravenous

The safety and efficacy of BENLYSTA was evaluated in an international, randomized, double‑blind, placebo‑controlled, 52‑week, pharmacokinetics (PK), efficacy and safety trial (Trial 6) conducted in 93 pediatric subjects with a clinical diagnosis of SLE according to the American College of Rheumatology classification criteria. Subjects had active SLE disease, defined as a SELENA-SLEDAI score ≥6 and positive autoantibodies at screening as defined in the adult trials. Subjects were on a stable SLE treatment regimen (standard of care) and had similar inclusion and exclusion criteria as in the adult studies. The median age was 15 years (range: 6 to 17). The majority (95%) of subjects were female. More than 50% of subjects had 3 or more active organ systems involved at baseline. The most common active organ systems at baseline based on SELENA-SLEDAI were mucocutaneous (91%), immunologic (74%), and musculoskeletal (73%). Overall, 19% of pediatric subjects had some degree of renal activity and less than 7% had activity in the cardio‑respiratory, hematologic, CNS or vascular systems. Randomization into age‑related treatment cohorts was stratified by screening SELENA-SLEDAI scores (6 to 12 vs >13) and age (5 to 11 years vs 12 to 17 years).

The primary efficacy endpoint was the SLE Responder Index (SRI-4) at Week 52, as described in the adult intravenous trials. There was a numerically higher proportion of pediatric subjects achieving a response in SRI‑4 and its components in pediatric subjects receiving BENLYSTA plus standard therapy compared with placebo plus standard therapy (Table 9).

Table 9. Response Rate at Week 52a in Pediatric Subjects 5 Years of Age and Older with Active SLE (Intravenous Treatment) (Trial 6)
Responseb | Placebo +; Standard Therapy; (n = 39) | BENLYSTA; 10 mg/kg +; Standard Therapy; (n = 53)
SLE Responder Index | 44% | 53%
Odds Ratio; (95% CI) vs. Placebo |  | 1.49; (0.64, 3.46)
Components of SLE Responder Index
Percent of subjects with reduction in SELENA‑SLEDAI ≥4 | 44% | 55%
Percent of subjects with no worsening by BILAG index | 62% | 74%
Percent of subjects with no worsening by PGA | 67% | 76%
Other Endpoints
SRI-6 using SELENA SLEDAI ≥6-point reduction | 34% | 41%
Proportion of subjects with a sustained SRI response | 41% | 43%
a Based on a non-powered trial.
b Analyses excluded any subject missing a baseline assessment for any of the components (1 for placebo).

Effect on Concomitant Steroid Treatment: At baseline, 95% of pediatric subjects were receiving prednisone. Among those pediatric subjects, 20% of pediatric subjects receiving BENLYSTA plus standard therapy reduced their average prednisone dose by at least 25% per day during Weeks 44 through 52 compared with 21% of pediatric subjects on placebo plus standard therapy.

Effect on Severe SLE Flares: In Trial 6, the probability of experiencing a severe SLE flare, as measured by the modified SELENA-SLEDAI Flare Index, excluding severe flares triggered only by an increase of the SELENA‑SLEDAI score to >12, was calculated. The proportion of pediatric subjects reporting at least one severe flare during the trial was numerically lower in pediatric subjects receiving BENLYSTA plus standard therapy (17%) compared with those receiving placebo plus standard therapy (35%). Pediatric subjects receiving BENLYSTA 10 mg/kg plus standard therapy had a 64% lower risk of experiencing a severe flare during the 52 weeks of observation, relative to the placebo plus standard therapy group. Of the pediatric subjects experiencing a severe flare, the median time to the first severe flare was 150 days in pediatric subjects receiving BENLYSTA plus standard therapy compared with 113 days in pediatric subjects receiving placebo plus standard therapy.

14.5 Subcutaneous Administration in Adults with Active SLE

Trial 7: Active SLE – BENLYSTA 200 mg - Subcutaneous

The safety and effectiveness of BENLYSTA administered subcutaneously were evaluated in a randomized, double‑blind, placebo‑controlled trial involving 836 adult subjects with SLE according to the American College of Rheumatology criteria (Trial 7, NCT01484496). Subjects with severe active lupus nephritis and severe active CNS lupus were excluded. The trial (2:1 randomization) evaluated BENLYSTA 200 mg once weekly plus standard therapy (n = 556) compared with placebo once weekly plus standard therapy (n = 280) over 52 weeks in subjects with active SLE disease. Subjects had to have a SELENA‑SLEDAI score of ≥8 and positive autoantibody test (anti‑nuclear antibody [ANA] and/or anti‑double–stranded DNA [anti‑dsDNA]) results at screening.

No significant differences in baseline subject characteristics were observed between treatment groups. In some countries, treatment with a B‑cell–targeted agent was permitted if received a year or more prior to baseline; otherwise, treatment with a B‑cell–targeted agent was not permitted. Subjects were excluded from the trial if they were currently receiving other biologic agents. Anti‑tumor necrosis factor therapy, intravenous cyclophosphamide, interleukin‑1 receptor antagonist, IVIG, prednisone >100 mg/day, and plasmapheresis were not permitted within the previous 3 months or during the trial. The trial was conducted in North America, South America, Europe, and Asia. Baseline concomitant medications included corticosteroids (86%), antimalarials (69%), and immunosuppressives (46%, including azathioprine, methotrexate, and mycophenolate). Most subjects (approximately 80%) were receiving 2 or more classes of SLE medications.

More than 50% of subjects had 3 or more active organ systems involved at baseline. The most common active organ systems at baseline based on SELENA‑SLEDAI were mucocutaneous (88%), musculoskeletal (78%), and immunologic (76%). Overall, 12% of subjects had some degree of renal activity and less than 15% of subjects had activity in the vascular, cardio‑respiratory, or CNS systems. Subjects were stratified by disease severity based on their SELENA‑SLEDAI score (≤9 vs. ≥10), complement level (C3 and/or C4 low vs. other), and race (Black vs. other), and then randomly assigned to receive BENLYSTA 200 mg plus standard therapy or placebo once weekly plus standard therapy.

The primary efficacy endpoint was the SLE Responder Index‑4 (SRI‑4) at Week 52 as described in the intravenous trials. Secondary efficacy endpoints included time to first severe flare (as measured by the modified SELENA‑SLEDAI SLE Flare Index) and the proportion of subjects receiving prednisone >7.5 mg/day at baseline whose average prednisone dose had been reduced by ≥25% to ≤7.5 mg/day during Weeks 40 through 52.

The proportion of subjects achieving an SRI‑4 response was significantly higher in subjects receiving BENLYSTA plus standard therapy compared with placebo plus standard therapy. The trends comparing the treatment groups with respect to the probability of response for the individual components of the endpoint were consistent with that of the SRI‑4 (Table 10).

Table 10. Clinical Response Rate in Adult Subjects with Active SLE after 52 Weeks of Subcutaneous Treatment (Trial 7)
Responsea | Placebo +; Standard Therapy; (n = 279) | BENLYSTA +; Standard Therapy; (n = 554)
SLE Responder Index-4 (SRI-4)b | 48% | 61%; P = 0.0006
Odds Ratio; (95% CI) vs. placebo |  | 1.7; (1.3, 2.3)
Components of SLE Responder Index-4 (SRI-4)
Percent of subjects with reduction in SELENA-SLEDAI ≥4 | 49% | 62%
Percent of subjects with no worsening by BILAG index | 74% | 81%
Percent of subjects with no worsening by PGA | 73% | 81%
a Analyses excluded any subject missing a baseline assessment for any of the components (1 for placebo; 2 for belimumab).
b Subjects dropping out of the trial early or experiencing certain increases in background medication were considered as failures in these analyses. A higher proportion of subjects receiving placebo plus standard therapy were considered as failures for this reason compared with the group receiving BENLYSTA plus standard therapy.

The reduction in disease activity seen in the SRI-4 was related primarily to improvement in the most commonly involved organ systems, namely, mucocutaneous, musculoskeletal, immunologic, and vascular.

The proportion of SRI-4 responders by visit through Week 52 is shown in Figure 3.

Figure 3. Proportion (%) of SRI-4 Responders (+/- Standard Error) by Visita (Subcutaneous Treatment in Adult Subjects with Active SLE) (Trial 7)

a The same subjects may not have responded at each timepoint.

Effect in Black/African‑American Subjects: Exploratory sub‑group analyses of SRI‑4 response rate in Black subjects (n = 91) were performed. The SRI‑4 response rate in Black subjects receiving BENLYSTA plus standard therapy was 45% (26/58) compared with 39% (13/33) in the group receiving placebo plus standard therapy [see Use in Specific Populations (8.8)].

Effect on Concomitant Steroid Treatment: At baseline, 60% of subjects were receiving prednisone at doses >7.5 mg/day. Among these subjects, 18% of subjects receiving BENLYSTA plus standard therapy reduced their average prednisone dose by at least 25% to ≤7.5 mg/day during Weeks 40 through 52 compared with 12% of subjects on placebo plus standard therapy; this difference was not statistically significant (OR = 1.65 [95% CI: 0.95, 2.84]).

Effect on Severe SLE Flares: The probability of experiencing a severe SLE flare, as measured by the modified SELENA‑SLEDAI SLE Flare Index, excluding severe flares triggered only by an increase of the SELENA‑SLEDAI score to >12, was calculated. The proportion of subjects reporting at least 1 severe flare during the trial was lower in subjects treated with BENLYSTA plus standard therapy (11%) compared with those receiving placebo plus standard therapy (18%). Subjects treated with BENLYSTA plus standard therapy had a 49% lower risk of experiencing at least 1 severe flare during the 52 weeks of observation, relative to the subjects receiving placebo plus standard therapy (HR = 0.51 [95% CI: 0.35, 0.74]). Of the subjects experiencing a severe flare, the median time to the first severe flare was delayed in subjects receiving BENLYSTA plus standard therapy compared with placebo plus standard therapy (171 days vs. 118 days).

16 HOW SUPPLIED/STORAGE AND HANDLING

16.1 Intravenous Infusion

BENLYSTA (belimumab) for injection is a sterile, preservative-free, lyophilized powder for reconstitution and dilution prior to intravenous infusion provided in single‑dose glass vials with a rubber stopper (not made with natural rubber latex) and a flip‑off seal. Each 5‑mL vial contains 120 mg of belimumab. Each 20‑mL vial contains 400 mg of belimumab.

BENLYSTA vials are supplied as follows:

120 mg belimumab in a 5‑mL single-dose vial (NDC 49401-101-01)

400 mg belimumab in a 20‑mL single-dose vial (NDC 49401-102-01)

Refrigerate vials at 36°F to 46°F (2°C to 8°C). Store vials in the original carton until use to protect from light. Do not freeze. Avoid exposure to heat.

16.2 Subcutaneous Injection

BENLYSTA (belimumab) injection is a clear to opalescent, and colorless to pale yellow solution for subcutaneous use. Each single-dose prefilled autoinjector or single-dose prefilled syringe is designed to deliver 200 mg of belimumab in 1 mL of solution and is supplied as follows:

200 mg/mL single-dose prefilled autoinjector with 27-gauge, half-inch needle attached (NDC 49401-088-01) in a carton of 4 (NDC 49401-088-35).

200 mg/mL single-dose prefilled glass syringe with 27-gauge, half-inch needle attached (NDC 49401-088-42) in a carton of 4 (NDC 49401-088-47).

Prior to Dispensing

Refrigerate prefilled autoinjectors and prefilled syringes at 36°F to 46°F (2°C to 8°C). Keep the product in the original carton to protect from light until the time of use. Do not freeze. Do not shake. Avoid exposure to heat.

Following Dispensing

Refrigerate prefilled autoinjectors and prefilled syringes at 36°F to 46°F (2°C to 8°C). Keep the product in the original carton to protect from light until the time of use. Do not freeze. Do not shake. Avoid exposure to heat.

BENLYSTA may be stored outside of the refrigerator up to 86°F (30°C) for up to 12 hours if protected from sunlight. Do not use and do not place back in refrigerator if left out for more than 12 hours.

17 PATIENT COUNSELING INFORMATION

Advise the patient to read the FDA-approved patient labeling (Medication Guide and Instructions for Use). It is important that the patient’s overall health be assessed at each visit and any questions resulting from the patient’s reading of the Medication Guide and Instructions for Use be discussed.

For patients receiving BENLYSTA, give patients the Medication Guide for BENLYSTA.

Serious Infections

Inform patients that BENLYSTA may decrease their ability to fight infections, and that serious infections, including some fatal ones, occurred in patients receiving BENLYSTA in clinical trials. Instruct patients to tell their healthcare provider if they develop signs or symptoms of an infection [see Warnings and Precautions (5.1)].

Progressive Multifocal Leukoencephalopathy

Advise patients to contact their healthcare professional if they experience new or worsening neurological symptoms such as memory loss, confusion, dizziness or loss of balance, difficulty talking or walking, or vision problems [see Warnings and Precautions (5.1)].

Hypersensitivity Reactions/Anaphylaxis

Educate patients on the signs and symptoms of hypersensitivity reactions and infusion-related reactions, including wheezing, difficulty breathing, angioedema, rash, hypotension, bradycardia, and headache. Instruct patients to immediately tell their healthcare provider if they experience symptoms of an allergic reaction during or after the administration of BENLYSTA. Inform patients about possible delayed reactions that may include a combination of symptoms such as rash, nausea, fatigue, muscle aches, headache, and/or facial swelling that may occur after administration of BENLYSTA and advise them to contact their healthcare provider [see Warnings and Precautions (5.2)].

Depression and Suicidality

Instruct patients (and caregivers if applicable) to contact their healthcare provider if they experience new or worsening depression, suicidal thoughts, or other mood changes [see Warnings and Precautions (5.3)].

Immunizations

Inform patients that they should not receive live vaccines while taking BENLYSTA. Response to vaccinations could be impaired by BENLYSTA [see Warnings and Precautions (5.5)].

Pregnancy Registry

Inform patients that there is a pregnancy registry to evaluate fetal outcomes of pregnant women with lupus exposed to BENLYSTA [see Use in Specific Populations (8.1)].

Pregnancy

Inform female patients of reproductive potential that BENLYSTA may impact the immune system in infants of treated mothers and to inform their prescriber of a known or suspected pregnancy [see Use in Specific Populations (8.1)].

Trademarks are owned by or licensed to the GSK group of companies.

Manufactured by GlaxoSmithKline LLC

Philadelphia, PA 19104, U.S. License No. 1727, and

Distributed by GlaxoSmithKline

Durham, NC 27701

©2025 GSK group of companies or its licensor.

BNL:21PI

DETACH HERE AND GIVE MEDICATION GUIDE TO PATIENT.

- - - - - - - - - - - - - - - - - - - - - - - - - - - - - - - - - - - - - - - - - - - - - - - - - - - - - - - - - - - - - - - - - - - - - - - - - -

MEDICATION GUIDE

BENLYSTA (ben-LIST-ah)

(belimumab)

for injection, for intravenous use

BENLYSTA (ben-LIST-ah)

(belimumab)

injection, for subcutaneous use

What is the most important information I should know about BENLYSTA?

Immunosuppressive agents, including BENLYSTA can cause serious side effects. Some of these side effects may cause death. The following are serious adverse reactions that have occurred in patients receiving BENLYSTA:

1. Infections. Infections could be serious, leading to hospitalization or death. Tell your healthcare provider right away if you have any of the following symptoms of an infection:

- fever
- chills
- pain or burning with urination

- urinating often
- coughing up mucus
- warm, red, or painful skin or sores on your body

2. Allergic (hypersensitivity) reactions. Serious allergic reactions can happen on the day of, or in the days after, receiving BENLYSTA and may cause death. Your healthcare provider will watch you closely while you are receiving BENLYSTA given in a vein (intravenous infusion) and after your infusion for signs of a reaction. Allergic reactions can sometimes be delayed. Tell your healthcare provider right away if you have any of the following symptoms of an allergic reaction following use of BENLYSTA:

- itching
- swelling of the face, lips, mouth, tongue, or throat
- trouble breathing
- anxiousness

- low blood pressure
- dizziness or fainting
- headache
- nausea
- skin rash

3. Mental health problems and suicide. Symptoms of mental health problems can occur. Tell your healthcare provider right away if you have any of the following symptoms:

- thoughts of suicide or dying
- attempt to commit suicide
- trouble sleeping (insomnia)
- new or worse anxiety

- new or worse depression
- acting on dangerous impulses
- other unusual changes in your behavior or mood
- thoughts of hurting yourself or others

What is BENLYSTA?

- BENLYSTA is a prescription medicine used to treat adults and children 5 years of age and older with:
○active systemic lupus erythematosus (SLE or lupus) who are receiving other lupus medicines, and
○active lupus nephritis (lupus‑related kidney inflammation), who are receiving other lupus medicines.
- BENLYSTA contains belimumab which is in a group of medicines called monoclonal antibodies. Lupus is a disease of the immune system (the body system that fights infection). When given together with other medicines for lupus, BENLYSTA decreases lupus disease activity more than other lupus medicines alone.
- It is not known if BENLYSTA is safe and effective in people with severe active central nervous system lupus.
- It is not known if BENLYSTA is safe and effective for use in children less than 5 years of age.
- It is not known if BENLYSTA, given under the skin (subcutaneously), is safe and effective for use in children who weigh less than 33 pounds (15 kilograms).

Do not use BENLYSTA if you:

- are allergic to belimumab or any of the ingredients in BENLYSTA. See the end of this Medication Guide for a complete list of ingredients in BENLYSTA.

Before you receive BENLYSTA, tell your healthcare provider about all of your medical conditions, including if you:

- think you have an infection or have infections that keep coming back. You should not receive BENLYSTA if you have an infection unless your healthcare provider tells you to. See “What is the most important information I should know about BENLYSTA?”
- have or have had mental health problems such as depression or thoughts of suicide.
- have recently received a vaccination or if you think you may need a vaccination. If you are receiving BENLYSTA, you should not receive live vaccines.
- are allergic to other medicines.
- are receiving other biologic medicines or monoclonal antibodies.
- have or have had any type of cancer.
- are pregnant or plan to become pregnant. It is not known if BENLYSTA will harm your unborn baby. You should talk to your healthcare provider about whether to prevent pregnancy while on BENLYSTA. If you choose to prevent pregnancy, you should use an effective method of birth control while receiving BENLYSTA and for at least 4 months after the final dose of BENLYSTA.
○ Tell your healthcare provider right away if you become pregnant during your treatment with BENLYSTA or if you think you may be pregnant.
○ If you become pregnant while receiving BENLYSTA, talk to your healthcare provider about enrolling in the BENLYSTA Pregnancy Registry. You can enroll in this registry by calling 1-877-311-8972 or go to https://mothertobaby.org/ongoing-study/benlysta-belimumab/. The purpose of this registry is to collect information about the health of you and your baby.
○ are breastfeeding or plan to breastfeed. It is not known if BENLYSTA passes into your breast milk. You and your healthcare provider should talk about whether or not you should receive BENLYSTA and breastfeed.

Tell your healthcare provider about all the medicines you take, including prescription and over-the-counter medicines, vitamins, and herbal supplements.

Know the medicines you take. Keep a list of your medicines with you to show to your healthcare provider and pharmacist when you get a new medicine.

How will I receive BENLYSTA?

When given in a vein (intravenously)

- You will be given BENLYSTA by a healthcare provider through a needle placed in a vein (IV infusion). It takes about 1 hour to give you the full dose of BENLYSTA.
- Your healthcare provider will tell you how often you should receive BENLYSTA.
- Your healthcare provider may give you medicines before you receive BENLYSTA to help reduce your chance of having a reaction. A healthcare provider will watch you closely while you are receiving BENLYSTA and after your infusion for signs of a reaction. A healthcare provider will review the signs and symptoms of possible allergic reactions that could happen after your infusion.

When given under the skin (subcutaneously)

- Your healthcare provider will tell you how often and how much of BENLYSTA you should use. Use BENLYSTA exactly as your healthcare provider tells you to.
- Read the Instructions for Use that comes with BENLYSTA for instructions about the right way to give your injections at home.
- BENLYSTA may be prescribed as a single‑dose autoinjector or as a single‑dose prefilled syringe.
○The single‑dose autoinjector is for use in adults and children 5 years of age and older.
○The single‑dose prefilled syringe is for use in adults 18 years of age and older.
- Before you use BENLYSTA, your healthcare provider will show you or your caregiver how to give the injections and review the signs and symptoms of possible allergic reactions.
- For children less than 10 years of age, BENLYSTA must be given by a healthcare provider or a trained caregiver.
- BENLYSTA is injected under the skin (subcutaneously) of your stomach (abdomen) or thigh.
- Use BENLYSTA on the same day each week or the same day every 2 weeks, as your healthcare provider tells you.
- If you miss your dose of BENLYSTA on your planned day, inject a dose as soon as you remember. Then, inject your next dose at your regularly scheduled time or continue dosing based on the new day injected. In case you are not sure when to inject BENLYSTA, call your healthcare provider.

What are the possible side effects of BENLYSTA?

BENLYSTA can cause serious side effects, including:

See “What is the most important information I should know about BENLYSTA?”

- Progressive multifocal leukoencephalopathy (PML). PML is a serious and life-threatening brain infection. Your chance of getting PML may be higher if you are treated with medicines that weaken your immune system, including BENLYSTA. PML can result in death or severe disability. If you notice any new or worsening medical problems such as those below, tell your healthcare provider right away:

○memory loss
○trouble thinking
○dizziness or loss of balance

○difficulty talking or walking
○loss of vision

- Cancer. BENLYSTA may reduce the activity of your immune system. Medicines that affect the immune system may increase your risk of certain cancers.

The most common side effects of BENLYSTA include:

○ nausea
○ diarrhea
○ fever
○stuffy or runny nose and sore throat (nasopharyngitis)
○ persistent cough (bronchitis)
○ trouble sleeping (insomnia)

○ leg or arm pain
○ depression
○ headache (migraine)
○ pain, redness, itching, or swelling at the site of injection (when given subcutaneously)

These are not all the possible side effects of BENLYSTA. Call your doctor for medical advice about side effects. You may report side effects to FDA at 1‑800‑FDA‑1088.

How should I store BENLYSTA?

- Store autoinjectors and prefilled syringes in the refrigerator at 36°F to 46°F (2°C to 8°C). Do not freeze.
- Keep BENLYSTA autoinjectors and prefilled syringes in the original package until time of use to protect from light.
- Do not shake. Keep away from heat and sunlight.
- Do not use and do not place back in the refrigerator if left out at room temperature for more than 12 hours.
- Safely throw away medicine that is out of date or no longer needed.

Keep BENLYSTA and all medicines out of the reach of children.

General information about the safe and effective use of BENLYSTA.

Medicines are sometimes prescribed for purposes other than those listed in a Medication Guide. Do not use BENLYSTA for a condition for which it was not prescribed. Do not give BENLYSTA to other people, even if they have the same symptoms that you have. It may harm them.

This Medication Guide summarizes the most important information about BENLYSTA. You can ask your healthcare provider or pharmacist for information about BENLYSTA that is written for health professionals.

What are the ingredients in BENLYSTA?

Active ingredient: belimumab.

Inactive ingredients (intravenous): citric acid, polysorbate 80, sodium citrate, sucrose.

Inactive Ingredients (subcutaneous): L-arginine hydrochloride, L-histidine, L-histidine monohydrochloride, polysorbate 80, sodium chloride.

For more information, go to www.BENLYSTA.com or call 1-877-423-6597.

Trademarks are owned by or licensed to the GSK group of companies.

Manufactured by GlaxoSmithKline LLC

Philadelphia, PA 19104, U.S. License No. 1727, and

Distributed by GlaxoSmithKline

Durham, NC 27701

©2025 GSK group of companies or its licensor.

BNL:16MG

This Medication Guide has been approved by the U.S. Food and Drug Administration. Revised: June 2025

INSTRUCTIONS FOR USE

BENLYSTA (ben-LIST-ah)
(belimumab)
injection, for subcutaneous use
Prefilled Syringe

Read These Sections First

Read this Instructions for Use before you start to use BENLYSTA and each time you refill your prescription. There may be new information. You should also receive training from your healthcare provider on how to use the prefilled syringe the right way. If you do not follow these instructions the prefilled syringe may not work properly. BENLYSTA is for use under the skin only (subcutaneous).

Important Storage Information

- Keep refrigerated until 30 minutes before use.
- Keep in the original package until time of use to protect from light.
- Do not freeze BENLYSTA. If the prefilled syringe has been frozen, do not use the prefilled syringe even if it is thawed.
- Keep away from heat and sunlight.
- Do not use and do not place back in the refrigerator if BENLYSTA is left out for more than 12 hours.
- Keep out of the reach of children.

Important Warnings

- The prefilled syringe should be used only 1 time and then thrown away. See below, “Step 6 - Throw away (dispose of) used syringe.”
○Do not share your BENLYSTA prefilled syringe with other people. You may give other people a serious infection or get a serious infection from them.
○Do not shake the prefilled syringe.
○Do not use if dropped onto a hard surface.
○Do not remove the Needle Cap until right before the injection.
○Do not use in children less than 18 years of age. It is not known if the prefilled syringe is safe and effective in children less than 18 years of age.

BENLYSTA Prefilled Syringe Parts

Before use

After Use – Needle is covered by Needle Guard

Supplies needed for the injection

BENLYSTA Prefilled Syringe

Alcohol Swab (not included)

Gauze Pad or Cotton Ball (not included)

Sharps Container (not included)

Step 1 Gather and check supplies

Gather supplies

- Remove 1 sealed tray containing a prefilled syringe from the refrigerator.
- Place any remaining prefilled syringes back into the refrigerator.
- Find a comfortable, well-lit, and clean surface and place the following supplies within reach:
○BENLYSTA Prefilled Syringe
○Alcohol swab (not included)
○Gauze pad or cotton ball (not included)
○Sharps container (not included)
- Do not give the injection if you do not have all the supplies listed.

Take out the prefilled syringe

- Peel back the film from the corner of the tray. See Figure A.

- Holding the middle of the prefilled syringe (near the inspection window), carefully take the prefilled syringe out of the tray. See Figure B.

Check expiration (Exp) date

- Check the expiration date on the prefilled syringe. See Figure C.

- Do not use if the expiration date has passed.

Step 2 Prepare and inspect the BENLYSTA Prefilled Syringe

Allow to come to room temperature

- Allow the prefilled syringe to sit at room temperature for 30 minutes. See Figure D.

○Do not warm the prefilled syringe in any other way. For example, do not warm in a microwave oven, hot water, or in direct sunlight.
○Do not remove the Needle Cap during this step.

Inspect BENLYSTA solution

- Look in the Inspection Window to check that the BENLYSTA solution is colorless to slightly yellow in color. See Figure E.

- It is normal to see 1 or more air bubbles in the solution.
- Do not use if the solution looks cloudy, discolored, or has particles.

Step 3 Choose and clean the injection site

Choose the injection site

- Choose where to inject (abdomen or thigh). See Figure F.
- If you need 2 injections to complete your dose, leave at least 2 inches between each injection if using the same site.
- Avoid injecting into the same site each time or in areas where the skin is tender, bruised, red, or hard.

- Do not inject within 2 inches of the belly button.

Clean the injection site

- Wash your hands.
- Clean the injection site by wiping it with an alcohol swab. Allow the skin to air dry. See Figure G.

- Do not touch this area again before giving the injection.
Step 4 Prepare for the injection
Remove the Needle Cap
- Do not remove the Needle Cap until right before you give the injection.
- Hold the prefilled syringe by the body and with the Needle facing away from you. Remove the Needle Cap by pulling it straight off. See Figure H.

- You may see a drop of liquid at the end of the Needle. This is normal.
- Do not let the Needle touch any surface.
- Do not push any air bubbles out of the prefilled syringe.
- Do not put the Needle Cap back onto the prefilled syringe.
- Keep your hands away from the Plunger to avoid pushing it before injecting.

Step 5 Inject BENLYSTA and inspect

Insert the Needle

- Hold the prefilled syringe in one hand and use your free hand to gently pinch the skin around the injection site. See Figure I.
- Insert the entire Needle into the pinched area of the skin at a slight 45-degree angle using a dart-like motion.

- After the Needle is completely inserted, release the pinched skin.

Complete the injection

- Push the Plunger all the way down until all of the solution is injected. See Figure J.

- While keeping your hold on the syringe, slowly move your thumb back, allowing the Plunger to rise up. The Needle will automatically rise up into the Needle Guard. See Figure K.

Inspect the injection site

- There may be a small amount of blood at the injection site. If needed, press a cotton ball or gauze pad on the injection site.
- Do not rub the injection site.

Step 6 Throw away (dispose of) used syringe

Dispose of the used syringe

Throw away (dispose of) the used syringe and Needle Cap in a Sharps Container. See Figure L.

- Put your used syringe and sharps in an FDA-cleared sharps disposal container right away after use. Do not throw away (dispose of) loose needles and syringes in your household trash.
- If you do not have an FDA-cleared sharps disposal container, you may use a household container that:
○is made of a heavy-duty plastic,
○can be closed with a tight-fitting, puncture-resistant lid, without sharps being able to come out,
○is upright and stable during use,
○is leak-resistant, and
○properly labeled to warn of hazardous waste inside the container.
- When your sharps disposal container is almost full, you will need to follow your community guidelines for the right way to dispose of your sharps disposal container. There may be state or local laws about how you should throw away used needles and syringes. For more information about safe sharps disposal, and for specific information about sharps disposal in the state that you live in, go to: http://www.fda.gov/safesharpsdisposal.
- Do not dispose of your used sharps disposal container in your household trash unless your community guidelines permit this. Do not recycle your used sharps disposal container.

Additional information

For more information about BENLYSTA, go to www.BENLYSTA.com or call 1-877-423-6597.

Trademarks are owned by or licensed to the GSK group of companies.

Manufactured by GlaxoSmithKline LLC

Philadelphia, PA 19104, U.S. License No. 1727, and

Distributed by GlaxoSmithKline

Durham, NC 27701

©2025 GSK group of companies or its licensor.

BNL:8IFU-S

This Instructions for Use has been approved by the U.S. Food and Drug Administration. Revised July 2025

INSTRUCTIONS FOR USE

BENLYSTA (ben-LIST-ah)
(belimumab)
injection, for subcutaneous use
Prefilled Autoinjector

Read These Sections First

Read this Instructions for Use before you start to use BENLYSTA and each time you refill your prescription. There may be new information. You should also receive training from your healthcare provider on how to use the autoinjector the right way. If you do not follow these instructions the autoinjector may not work properly. BENLYSTA is for use under the skin only (subcutaneous).

Important Storage Information

- Keep refrigerated until 30 minutes before use.
- Keep in the original package until time of use to protect from light.
- Do not freeze BENLYSTA. If the autoinjector has been frozen, do not use the autoinjector even if it is thawed.
- Keep away from heat and sunlight.
- Do not use and do not place back in the refrigerator if BENLYSTA is left out for more than 12 hours.
- Keep out of the reach of children.

Important Warnings

- The autoinjector should be used only 1 time and then thrown away. See below, “Step 6 – Throw away (dispose of) used autoinjector.”
○Do not share your BENLYSTA Autoinjector with other people. You may give other people a serious infection or get a serious infection from them.
○Do not shake the autoinjector.
○Do not use if dropped onto a hard surface.
○Do not remove the Ring Cap until right before the injection.
○For children less than 10 years of age, BENLYSTA must be given by a healthcare provider or a trained caregiver.

BENLYSTA Autoinjector Parts

Supplies needed for the injection

BENLYSTA Autoinjector

Alcohol Swab (not included)

Gauze Pad or Cotton Ball (not included)

Sharps Container (not included)

Step 1 Gather and check supplies

Gather supplies

- Remove 1 sealed tray containing an autoinjector from the refrigerator.
- Place any remaining autoinjectors back into the refrigerator.
- Find a comfortable, well-lit, and clean surface and place the following supplies within reach:
○BENLYSTA Autoinjector
○Alcohol swab (not included)
○Gauze pad or cotton ball (not included)
○Sharps container (not included)
- Do not give the injection if you do not have all the supplies listed.

Take out the autoinjector

- Peel back the film from the corner of the tray. See Figure A.

- Holding the middle of the autoinjector (near the inspection window), carefully take the autoinjector out of the tray. See Figure B.

Check expiration (Exp) date

- Check the expiration date on the autoinjector. See Figure C.

- Do not use if the expiration date has passed.

Step 2 Prepare and inspect the BENLYSTA Autoinjector

Allow to come to room temperature

- Allow the autoinjector to sit at room temperature for 30 minutes. See Figure D.

○Do not warm the autoinjector in any other way. For example, do not warm in a microwave oven, hot water, or in direct sunlight.
○Do not remove the Ring Cap during this step.

Inspect BENLYSTA solution

- Look in the Inspection Window to check that the BENLYSTA solution is colorless to slightly yellow in color. See Figure E.

- It is normal to see 1 or more air bubbles in the solution.
- Do not use if the solution looks cloudy, discolored, or has particles.

Step 3 Choose and clean the injection site

Choose the injection site

- Choose where to inject (abdomen or thigh). See Figure F.
- If you need 2 injections to complete your dose, leave at least 2 inches between each injection if using the same site.
- Avoid injecting into the same site each time or in areas where the skin is tender, bruised, red, or hard.

- Do not inject within 2 inches of the belly button.

Clean the injection site

- Wash your hands.
- Clean the injection site by wiping it with an alcohol swab. Allow the skin to air dry. See Figure G.

- Do not touch this area again before giving the injection.

Step 4 Prepare for the injection

Remove the Ring Cap

- Do not remove the Ring Cap until right before you give the injection.
- Remove the Ring Cap by pulling or twisting it off. The Ring Cap may be twisted off in either a clockwise or counterclockwise direction. See Figure H.

- Do not put the Ring Cap back onto the autoinjector.

Position the autoinjector

- Hold the autoinjector comfortably so that you can see the Inspection Window. It is important that you can look at the Inspection Window while giving the injection. You will look at the Inspection Window to:
○see that the purple indicator is moving while you are injecting.
○see that the purple indicator has stopped to make sure that the dose is complete. See Figure I.

- Position the autoinjector straight over the injection site at a 90-degree angle. Make sure the Gold Needle Guard is flat on the skin.

Step 5 Inject BENLYSTA and inspect

Start the injection

- Firmly press the autoinjector all the way down onto the injection site and hold in place. See Figure J.
- This will insert the needle and start the injection.

- You may hear a “first click” at the start of the injection and see the Purple Indicator start to move through the Inspection Window. See Figure K.

Complete the injection

- Continue to hold the autoinjector down until you see that the Purple Indicator has stopped moving.
- You may hear a "second click" a few seconds before the Purple Indicator stops moving. See Figure L.

- The injection may take up to 15 seconds to complete.
- When the injection is complete, lift the autoinjector from the injection site.

Inspect the injection site

- There may be a small amount of blood at the injection site. If needed, press a cotton ball or gauze pad on the injection site.
○Do not rub the injection site

Step 6 Throw away (dispose of) used autoinjector

Dispose of the used autoinjector

- Throw away (dispose of) the used autoinjector and Ring Cap in a Sharps Container. See Figure M.
- Put your used autoinjector in an FDA-cleared sharps disposal container right away after use. Do not throw away (dispose of) in your household trash.
- If you do not have an FDA-cleared sharps disposal container, you may use a household container that:
○is made of a heavy-duty plastic,
○can be closed with a tight-fitting, puncture-resistant lid, without sharps being able to come out,
○is upright and stable during use,
○is leak-resistant, and
○properly labeled to warn of hazardous waste inside the container.
- When your sharps disposal container is almost full, you will need to follow your community guidelines for the right way to dispose of your sharps disposal container. There may be state or local laws about how you should throw away used needles and syringes. For more information about safe sharps disposal, and for specific information about sharps disposal in the state that you live in, go to: http://www.fda.gov/safesharpsdisposal.
- Do not dispose of your used sharps disposal container in your household trash unless your community guidelines permit this. Do not recycle your used sharps disposal container.

Additional information

For more information about BENLYSTA, go to www.BENLYSTA.com or call 1-877-423-6597.

Trademarks are owned by or licensed to the GSK group of companies.

Manufactured by GlaxoSmithKline LLC

Philadelphia, PA 19104, U.S. License No. 1727, and

Distributed by GlaxoSmithKline

Durham, NC 27701

©2025 GSK group of companies or its licensor.

BNL:7IFU-A

This Instructions for Use has been approved by the U.S. Food and Drug Administration. Revised July 2025

PACKAGE LABEL

PRINCIPAL DISPLAY PANEL

NDC 49401-101-01

Benlysta

(belimumab)

for Injection

120 mg/vial

GSK

For Intravenous Infusion after dilution only. Single-dose vial.

Discard unused portion

Reconstitution: Reconstitute with 1.5 mL of Sterile Water for Injection, USP. After reconstitution, the concentration of BENLYSTA is 80 mg/mL.

Dilution: Further dilute to 250 mL of one of the following solutions before use:

- 0.9% Sodium Chloride Injection, USP
- 0.45% Sodium Chloride Injection, USP
- Lactated Ringer’s Injection, USP

Federal Law requires dispensing of BENLYSTA with the Medication Guide provided with this carton.

Rx only

©2022 GSK group of companies or its licensor.

Rev. 9/22

62000000082255

PACKAGE LABEL

PRINCIPAL DISPLAY PANEL

NDC 49401-102-01

Benlysta

(belimumab)

for Injection

400 mg/vial

GSK

For Intravenous Infusion after dilution only. Single-dose vial.

Discard unused portion.

Reconstitution: Reconstitute with 4.8 mL of Sterile Water for Injection, USP. After reconstitution, the concentration of BENLYSTA is 80 mg/mL.

Dilution: Further dilute to 250 mL of one of the following solutions before use:

- 0.9% Sodium Chloride Injection, USP
- 0.45% Sodium Chloride Injection, USP
- Lactated Ringer’s Injection, USP

Federal Law requires dispensing of BENLYSTA with the Medication Guide provided with this carton.

Rx only

©2022 GSK group of companies or its licensor.

Rev. 9/22

62000000082242

PACKAGE LABEL

PRINCIPAL DISPLAY PANEL

NDC 49401-088-35

Benlysta

(belimumab)

Injection

200 mg/mL

Rx only

GSK

For Subcutaneous Use

Contents:

- 4 Single-Dose 1-mL Prefilled Autoinjectors
- Instructions for Use (Read carefully)
- Medication Guide
- Prescribing Information

Federal Law requires dispensing of BENLYSTA with the Medication Guide provided with this package.

©2024 GSK group of companies or is licensor.

Rev. 8/24

62000000095407